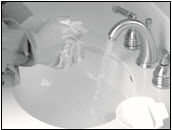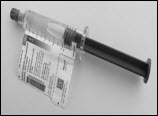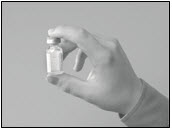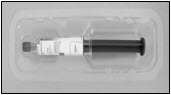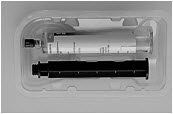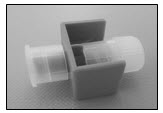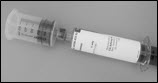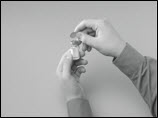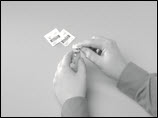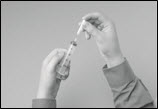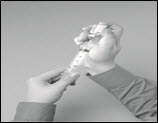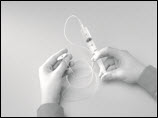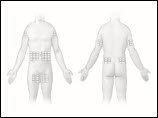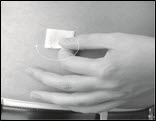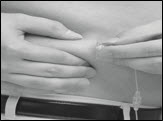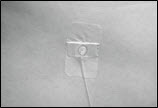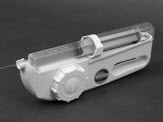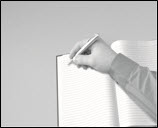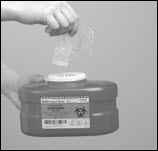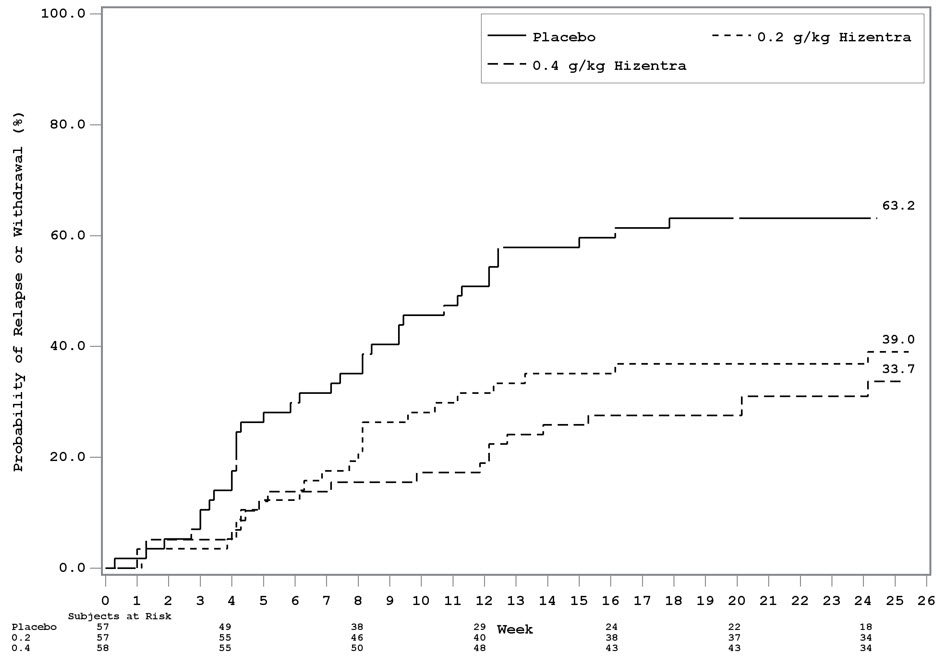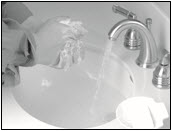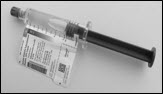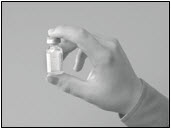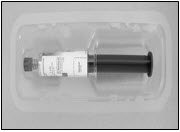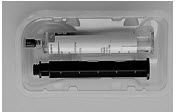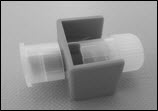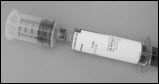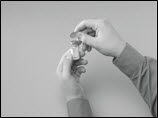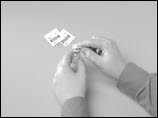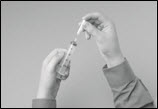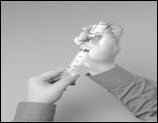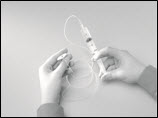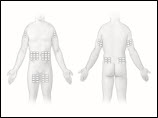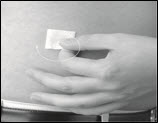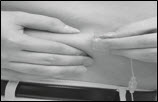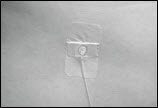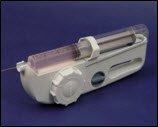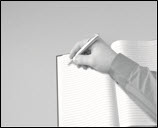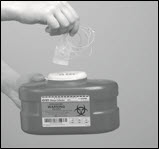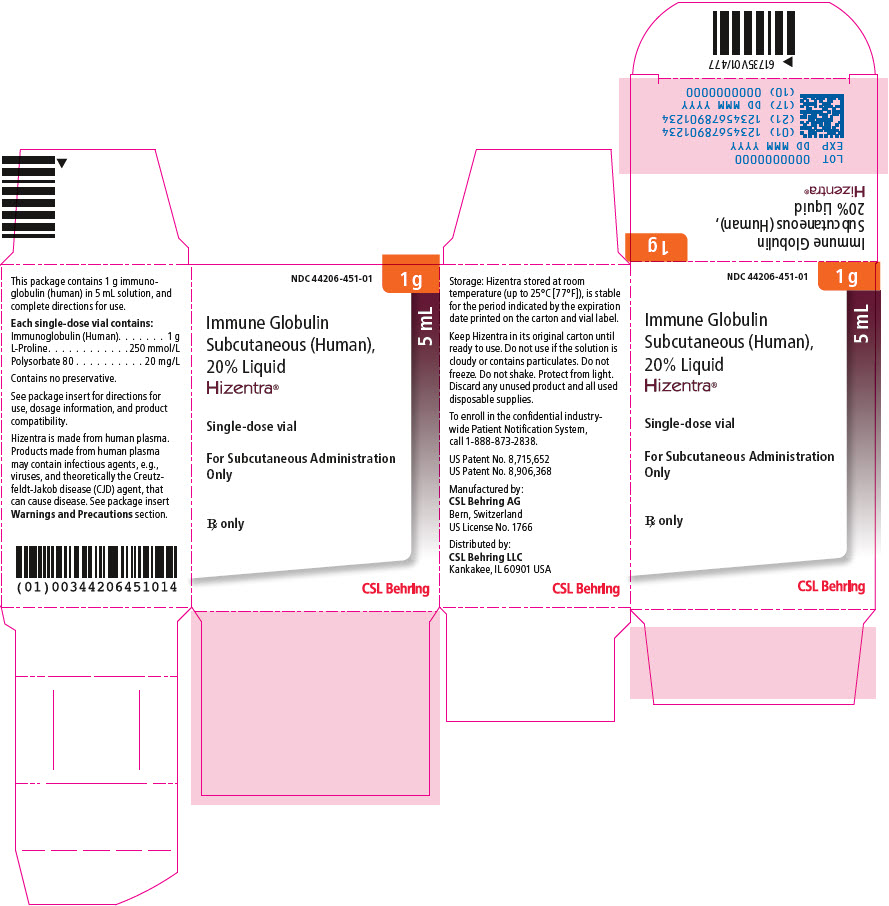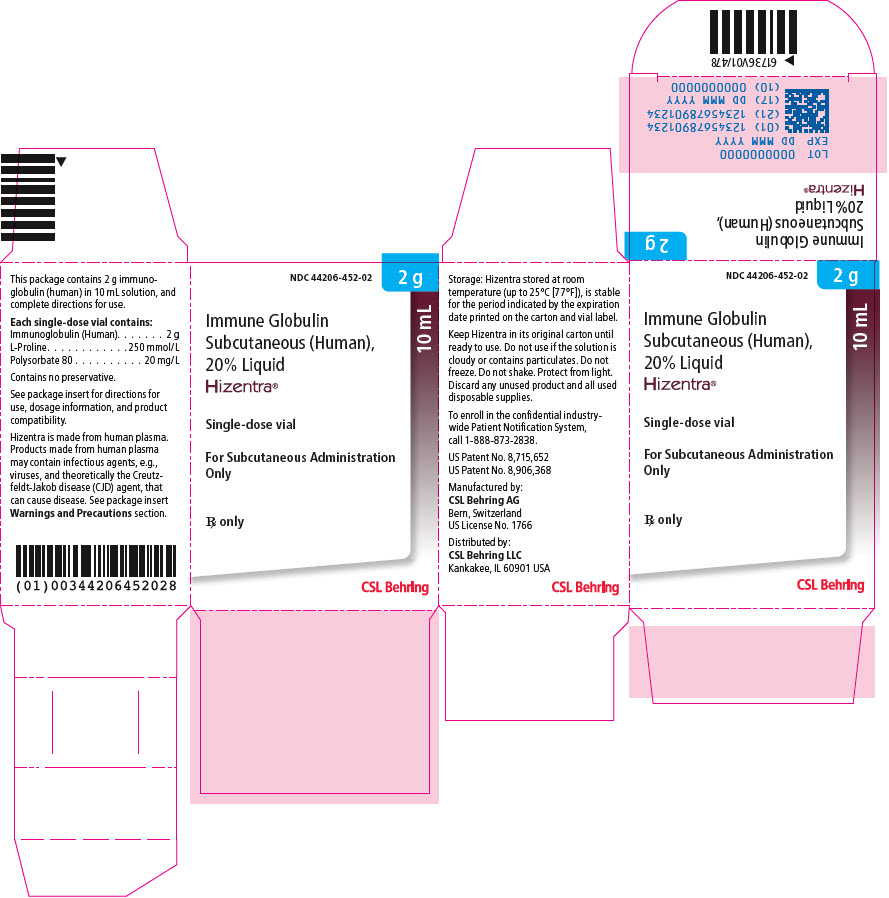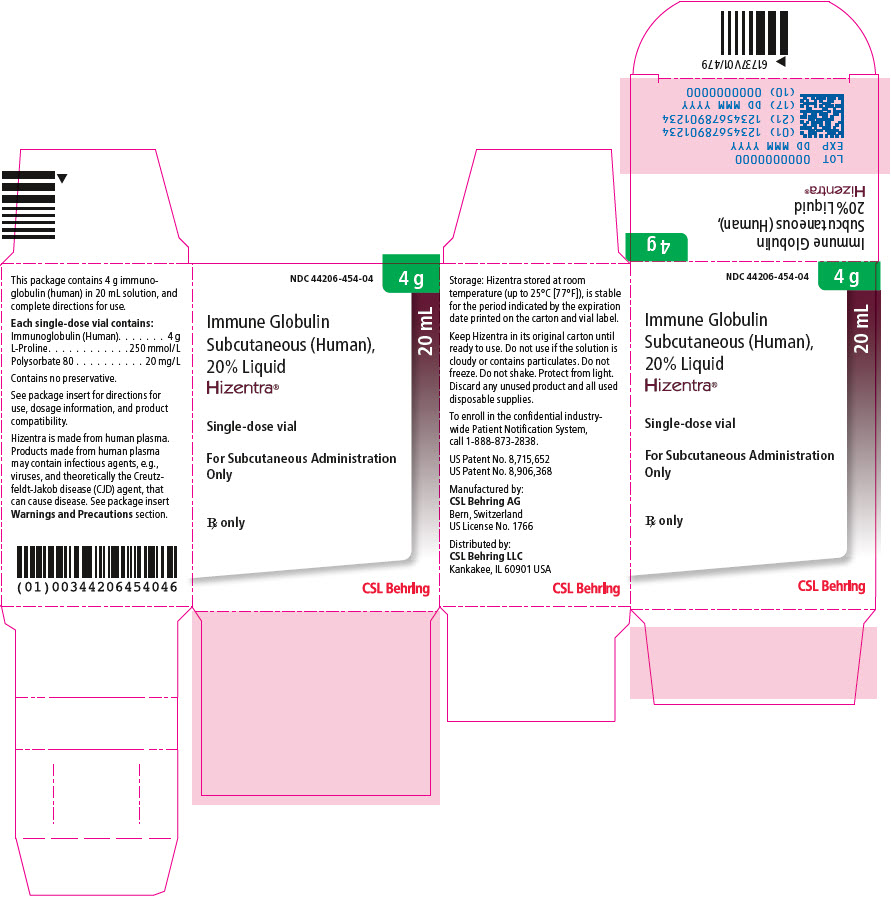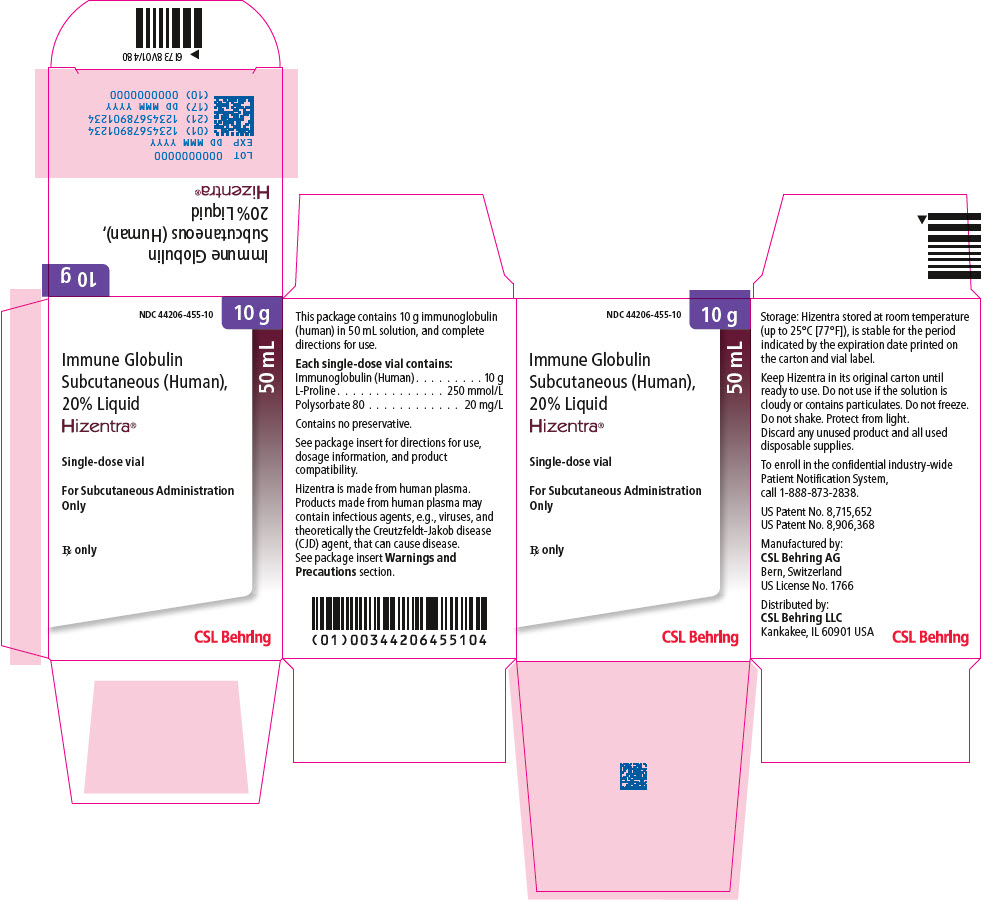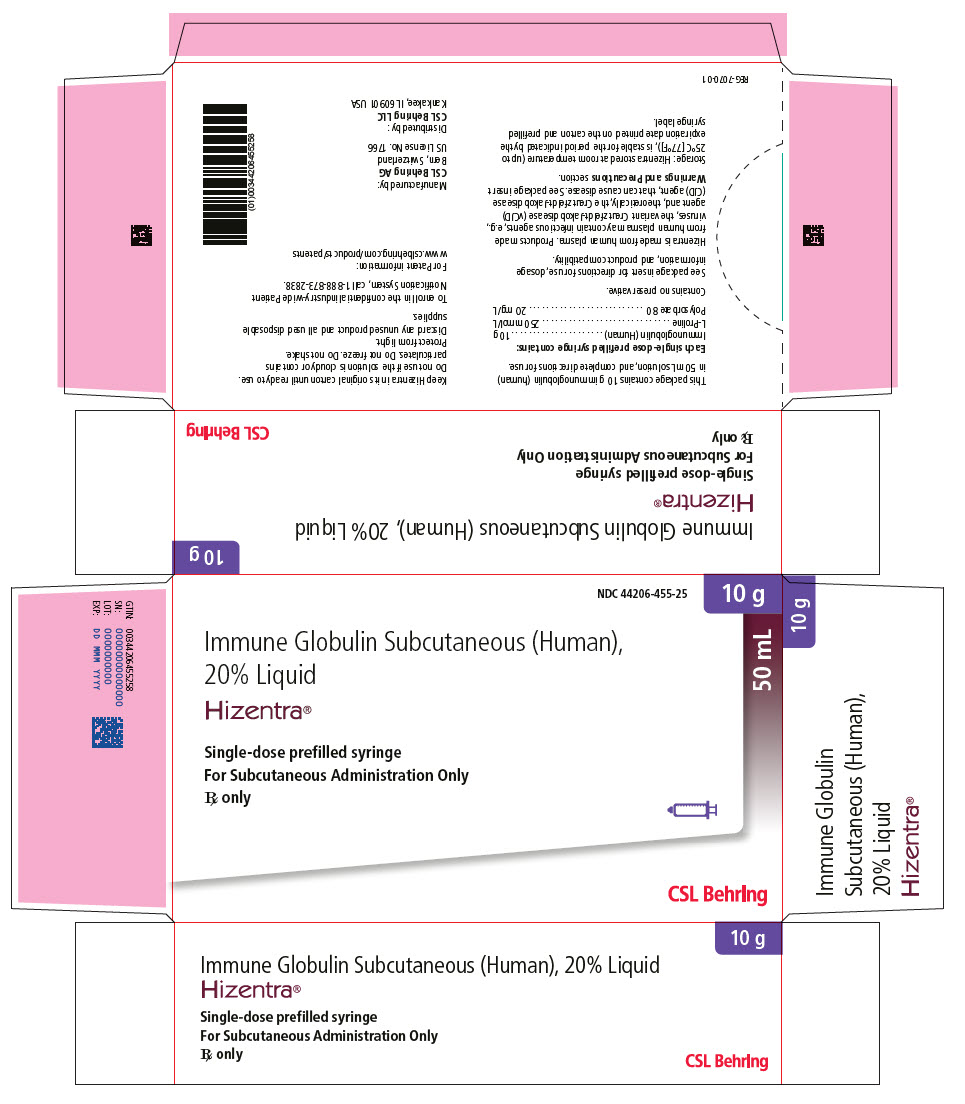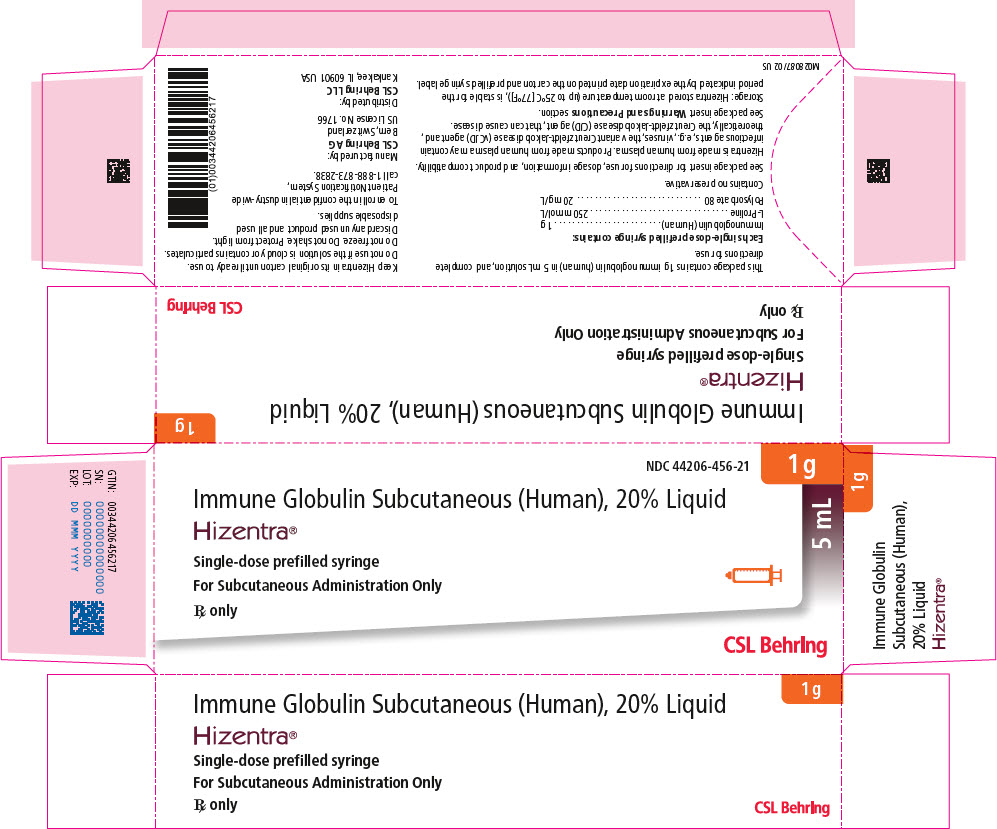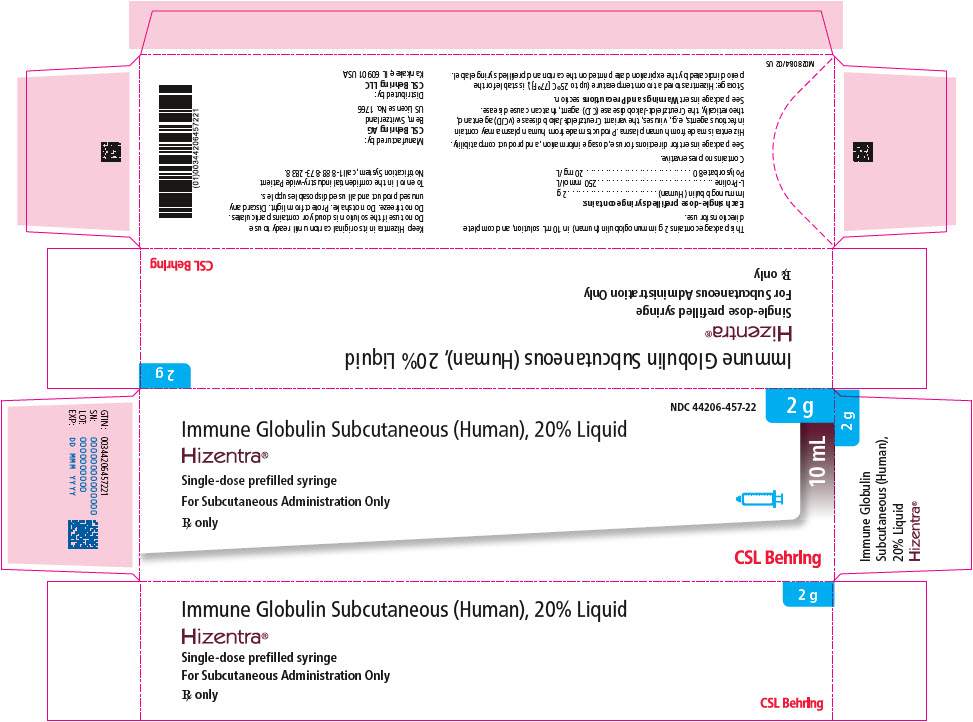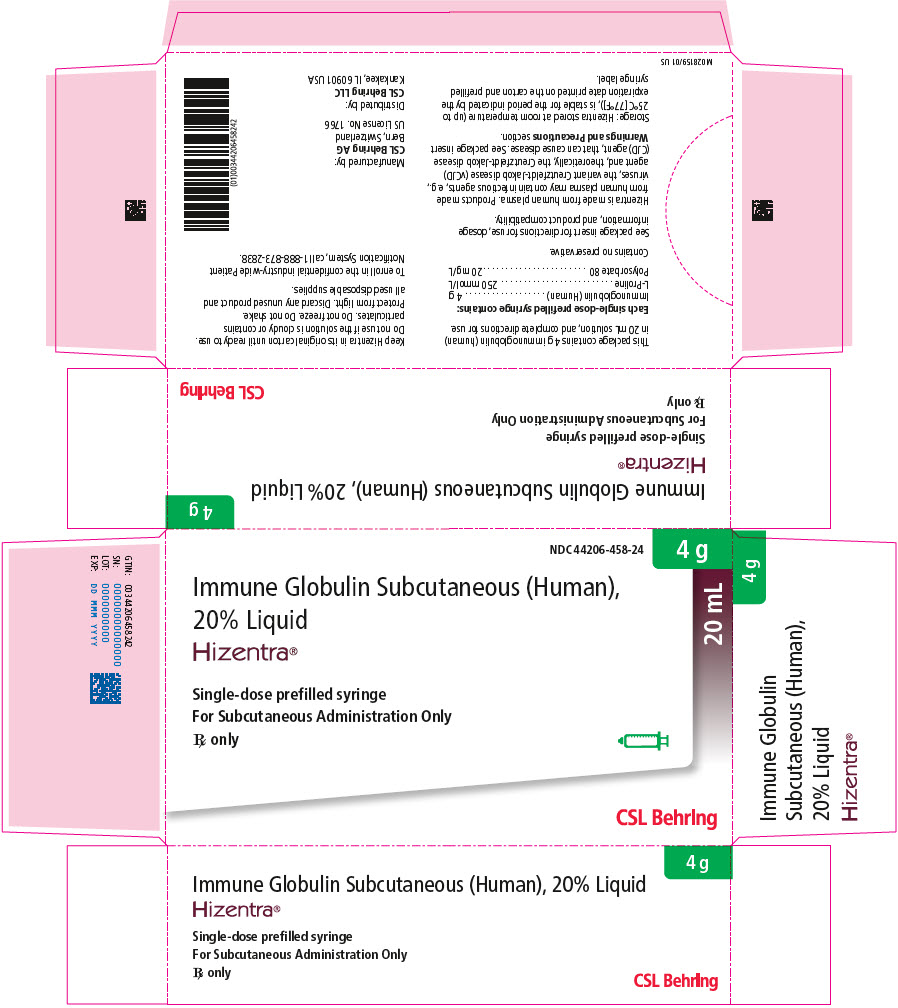 DRUG LABEL: Hizentra
NDC: 44206-451 | Form: LIQUID
Manufacturer: CSL Behring AG
Category: other | Type: PLASMA DERIVATIVE
Date: 20230420

ACTIVE INGREDIENTS: HUMAN IMMUNOGLOBULIN G 0.2 g/1 mL
INACTIVE INGREDIENTS: PROLINE; POLYSORBATE 80; HUMAN IMMUNOGLOBULIN A

HIGHLIGHTS OF PRESCRIBING INFORMATION

These highlights do not include all the information needed to use HIZENTRA® safely and effectively. See full prescribing information for HIZENTRA.
HIZENTRA, Immune Globulin Subcutaneous (Human), 20% Liquid
Initial U.S. Approval: 2010

WARNING: THROMBOSIS

See full prescribing information for complete boxed warning.

- Thrombosis may occur with immune globulin products, including HIZENTRA. Risk factors may include: advanced age, prolonged immobilization, hypercoagulable conditions, history of venous or arterial thrombosis, use of estrogens, indwelling vascular catheters, hyperviscosity, and cardiovascular risk factors.
- For patients at risk of thrombosis, administer HIZENTRA at the minimum dose and infusion rate practicable. Ensure adequate hydration in patients before administration. Monitor for signs and symptoms of thrombosis and assess blood viscosity in patients at risk for hyperviscosity.

RECENT MAJOR CHANGES

Dosage and Administration (2.3) | 04/2023

1 INDICATIONS AND USAGE

HIZENTRA is an Immune Globulin Subcutaneous (Human) (IGSC), 20% Liquid indicated for the treatment of:

- Primary immunodeficiency (PI) in adults and pediatric patients 2 years of age and older. (1.1)
- Maintenance therapy in adults with chronic inflammatory demyelinating polyneuropathy (CIDP). (1.2)

2 DOSAGE AND ADMINISTRATION

For subcutaneous infusion only.

Dose (2.2)

PI

Before switching to HIZENTRA, obtain the patient's serum IgG trough level to guide subsequent dose adjustments.

- Weekly: Start HIZENTRA 1 week after last Immune Globulin Intravenous (Human) (IGIV) infusion.

Initial weekly dose = | Previous IGIV dose (in grams) × 1.37
 | No. of weeks between IGIV doses

- Biweekly (every 2 weeks): Start HIZENTRA 1 or 2 weeks after the last IGIV infusion or 1 week after the last weekly IGSC infusion. Administer twice the calculated weekly dose.
- Frequent dosing (2 to 7 times per week): Start HIZENTRA 1 week after the last IGIV or IGSC infusion. Divide the calculated weekly dose by the desired number of times per week.
- Adjust the dose based on clinical response and serum IgG trough levels.

CIDP

- Initiate therapy with HIZENTRA 1 week after the last IGIV infusion.
- Recommended subcutaneous dose is 0.2 g/kg (1 mL/kg) body weight per week.
  - In the clinical study after transitioning from IGIV to HIZENTRA, a dose of 0.4 g/kg (2 mL/kg) body weight per week was also safe and effective to prevent CIDP relapse.
- If CIDP symptoms worsen, on 0.2 g/kg (1 mL/kg) body weight per week, consider increasing the HIZENTRA dose from 0.2 g/kg to 0.4 g/kg body weight per week.
  - If CIDP symptoms worsen on 0.4 g/kg body weight per week, consider re-initiating therapy with IGIV, while discontinuing HIZENTRA.
- Monitor patient's clinical response and adjust duration of therapy based on patient need.

Administration (2.3)

- PI: Administer at regular intervals from daily up to every 2 weeks.
- CIDP: Administer weekly.
- Infusion sites – Up to 8 infusion sites are allowed simultaneously, with at least 2 inches between sites.

Administration in PI
Infusion Parameters [As tolerated] | 1st Infusion | Subsequent Infusions
Volume (mL/site) | ≤15 | ≤25
Rate (mL/hr/site) | ≤15 | ≤25

Administration in CIDP
Infusion Parameters [As tolerated] | 1st Infusion | Subsequent Infusions
Volume (mL/site) | ≤20 | ≤50
Rate (mL/hr/site) | ≤20 | ≤50

3 DOSAGE FORMS AND STRENGTHS

0.2 g per mL (20%) protein solution for subcutaneous infusion available in a single-dose prefilled syringe (5 mL, 10 mL, 20 mL, and 50 mL) or tamper-evident vial (5 mL, 10 mL, 20 mL and 50 mL). (3)

4 CONTRAINDICATIONS

- Anaphylactic or severe systemic reaction to human immune globulin or inactive ingredients of HIZENTRA, such as polysorbate 80. (4)
- Hyperprolinemia Type I or II (HIZENTRA contains stabilizer L-proline). (4)
- IgA-deficient patients with antibodies against IgA and a history of hypersensitivity. (4)

5 WARNINGS AND PRECAUTIONS

- IgA-deficient patients with anti-IgA antibodies are at greater risk of severe hypersensitivity and anaphylactic reactions. (5.1)
- Thrombosis may occur following treatment with immune globulin products, including HIZENTRA. (5.2)
- Aseptic meningitis syndrome has been reported with IGIV or IGSC, including HIZENTRA treatment. (5.3)
- Monitor renal function, including blood urea nitrogen, serum creatinine, and urine output in patients at risk of acute renal failure. (5.4)
- Monitor for clinical signs and symptoms of hemolysis. (5.5)
- Monitor for pulmonary adverse reactions (transfusion-related acute lung injury [TRALI]). (5.6)
- HIZENTRA is made from human blood and may contain infectious agents, e.g., viruses, the variant Creutzfeldt-Jakob disease (vCJD) agent and, theoretically, the Creutzfeldt-Jakob disease (CJD) agent. (5.7)

6 ADVERSE REACTIONS

The most common adverse reactions observed in ≥5% of study subjects were local infusion site reactions, headache, diarrhea, fatigue, back pain, nausea, pain in extremity, cough, upper respiratory tract infection, rash, pruritus, vomiting, abdominal pain (upper), migraine, arthralgia, pain, fall and nasopharyngitis. (6)

To report SUSPECTED ADVERSE REACTIONS, contact CSL Behring Pharmacovigilance at 1-866-915-6958 or FDA at 1-800-FDA-1088 or www.fda.gov/medwatch.

7 DRUG INTERACTIONS

The passive transfer of antibodies may interfere with the response to live virus vaccines (7.1), and lead to misinterpretation of the results of serological testing. (5.8, 7.2)

FULL PRESCRIBING INFORMATION

WARNING: THROMBOSIS

- Thrombosis may occur with immune globulin products^1-3, including HIZENTRA. Risk factors may include: advanced age, prolonged immobilization, hypercoagulable conditions, history of venous or arterial thrombosis, use of estrogens, indwelling central vascular catheters, hyperviscosity, and cardiovascular risk factors. Thrombosis may occur in the absence of known risk factors [see Warnings and Precautions (5.2), and Patient Counseling Information (17).
- For patients at risk of thrombosis, administer HIZENTRA at the minimum dose and infusion rate practicable. Ensure adequate hydration in patients before administration. Monitor for signs and symptoms of thrombosis and assess blood viscosity in patients at risk for hyperviscosity [see Warnings and Precautions (5.2)].

1 INDICATIONS AND USAGE

HIZENTRA is an Immune Globulin Subcutaneous (Human) (IGSC), 20% Liquid indicated for the treatment of the following conditions:

1.1 Primary Immunodeficiency (PI)

HIZENTRA is indicated as replacement therapy for primary humoral immunodeficiency (PI) in adults and pediatric patients 2 years of age and older. This includes, but is not limited to, the humoral immune defect in congenital agammaglobulinemia, common variable immunodeficiency, X-linked agammaglobulinemia, Wiskott-Aldrich syndrome, and severe combined immunodeficiencies.

1.2 Chronic Inflammatory Demyelinating Polyneuropathy (CIDP)

HIZENTRA is indicated for the treatment of adult patients with chronic inflammatory demyelinating polyneuropathy (CIDP) as maintenance therapy to prevent relapse of neuromuscular disability and impairment.

Limitations of Use:

HIZENTRA maintenance therapy in CIDP has been systematically studied for 6 months and for a further 12 months in a follow-up study. Maintenance therapy beyond these periods should be individualized based upon the patient's response and need for continued therapy [see Dosage and Administration (2)].

2 DOSAGE AND ADMINISTRATION

For subcutaneous infusion only.

2.1 Preparation and Handling

HIZENTRA is a clear and pale yellow to light brown solution. Do not use if the solution is cloudy or contains particulates.

- Prior to administration, visually inspect each prefilled syringe or vial of HIZENTRA for particulate matter or discoloration, whenever the solution and container permit.
- Do not freeze. Do not use any solution that has been frozen.
- Check the product expiration date on the prefilled syringe or vial label. Do not use beyond the expiration date.
- Do not mix HIZENTRA with other products.
- Do not shake the prefilled syringe or vial.
- Use aseptic technique when preparing and administering this product.
- Both the HIZENTRA prefilled syringe and vial are single-dose containers. Multiple HIZENTRA prefilled syringes or vials can be administered to achieve the prescribed dose. Discard all used administration supplies and any unused product immediately after each infusion in accordance with local requirements.

2.2 Dose

Primary Immunodeficiency (PI)

- HIZENTRA can be administered at regular intervals from daily up to every 2 weeks (biweekly).
- Individualize the dose based on the patient's clinical response to HIZENTRA therapy and serum immunoglobulin G (IgG) trough levels.
- Before receiving treatment with HIZENTRA:
  - Ensure that patients have received Immune Globulin Intravenous (Human) (IGIV) treatment at regular intervals for at least 3 months.
  - Obtain the patient's serum IgG trough level to guide subsequent dose adjustments (see below, under Dose Adjustment).

Dosage for patients switching to HIZENTRA from IGIV

- Establish the initial weekly dose of HIZENTRA by converting the monthly IGIV dose into a weekly equivalent and increasing it using the dose adjustment factor. The goal is to achieve a systemic serum IgG exposure (area under the concentration-time curve [AUC]) not inferior to that of the previous IGIV treatment.
  - To calculate the initial weekly dose of HIZENTRA, divide the previous IGIV dose in grams by the number of weeks between doses during the patient's IGIV treatment (e.g., 3 or 4); then multiply this by the dose adjustment factor of 1.37 [see Clinical Pharmacology (12.3, Table 9)].
    Initial HIZENTRA dose | = Previous IGIV dose (in grams) × 1.37
     | Number of weeks between IGIV doses
  - To convert the HIZENTRA dose (in grams) to milliliters (mL), multiply the calculated dose (in grams) by 5.
- Provided the total weekly dose is maintained, any dosing interval from daily up to biweekly can be used and will result in systemic serum IgG exposure that is comparable to the previous IGIV or weekly HIZENTRA treatment [see Clinical Pharmacology (12.3)].
- For biweekly dosing, multiply the calculated HIZENTRA weekly dose by 2.
- For frequent dosing (2 to 7 times per week), divide the calculated weekly dose by the desired number of times per week (e.g., for 3 times per week dosing, divide weekly dose by 3).

Dosage for patients switching to HIZENTRA from IGSC

- The previous weekly IGSC dose should be maintained.
- For biweekly dosing, multiply the previous weekly dose by 2.
- For frequent dosing (2 to 7 times per week), divide the previous weekly dose by the desired number of times per week (e.g., for 3 times per week dosing, divide weekly dose by 3).

Start HIZENTRA treatment

- For weekly or frequent dosing, start treatment with HIZENTRA 1 week after the patient's last IGIV infusion or IGSC infusion.
- For biweekly dosing, start treatment 1 or 2 weeks after the last IGIV infusion or 1 week after the last weekly IGSC infusion.

Dose Adjustment

The dose may need to be adjusted to achieve the desired clinical response and serum IgG trough level, irrespective of the frequency of administration.

To determine if a dose adjustment should be considered, measure the patient's serum IgG trough level 2 to 3 months after switching to HIZENTRA.

Weekly dosing: When switching from IGIV to weekly HIZENTRA dosing, the target serum IgG trough level is projected to be approximately 16% higher than the last trough level during prior IGIV therapy [see Clinical Pharmacology (12.3)].

Biweekly dosing: When switching from IGIV to biweekly HIZENTRA dosing, the target serum IgG trough level is projected to be approximately 10% higher than the last IGIV trough level. When switching from weekly to biweekly dosing, the target trough is projected to be approximately 5% lower than the last trough level on weekly therapy [see Clinical Pharmacology (12.3)].

Frequent dosing: When switching from weekly dosing to more frequent dosing, the target serum IgG trough level is projected to be approximately 3 to 4% higher than the last trough level on weekly therapy [see Clinical Pharmacology (12.3)].

To adjust the dose based on serum trough levels, calculate the difference (in mg/dL) between the patient's IgG trough level obtained 2 to 3 months following the switch from IGIV or the last IGSC dose adjustment and the target IgG trough level for weekly or biweekly dosing. Then find this difference in Table 1 (Column 1) and, based on the HIZENTRA dosing frequency (for weekly or biweekly) and the patient's body weight, locate the corresponding adjustment amount (in mL) by which to increase (or decrease) the dose. For frequent dosing, add the weekly increment from Table 1 to the weekly-equivalent dose and then divide by the number of days of dosing.

Use the patient's clinical response as the primary consideration in dose adjustment. Additional dosage increments may be indicated based on the patient's clinical response (infection frequency and severity).

Table 1. Incremental Adjustment (mL) [Incremental adjustments based on slopes of the pharmacometric model-predicted relationship between serum IgG trough level and HIZENTRA dose increments of 1 mg/kg per week.] of the HIZENTRA Dose [Includes biweekly, weekly or frequent dosing.] Based on the Difference (±mg/dL) from the Target Serum IgG Trough Level
Difference From Target Serum IgG Trough Level (mg/dL) | Dosing Frequency | Weight Adjusted Dose Increment (mL)
Difference From Target Serum IgG Trough Level (mg/dL) | Dosing Frequency | Weight Group
Difference From Target Serum IgG Trough Level (mg/dL) | Dosing Frequency | >10 to ≤30 kg | >30 to ≤50 kg | >50 to ≤70 kg | >70 to ≤90 kg | >90 kg
50 | Weekly [To determine the dose increment for frequent dosing, add the weekly increment to the weekly-equivalent dose and then divide by the number of days of dosing.] | n/a | 2.5 | 5 | 5 | 10
50 | Biweekly | 5 | 5 | 10 | 10 | 20
100 | Weekly | 2.5 | 5 | 10 | 10 | 15
100 | Biweekly | 5 | 10 | 20 | 20 | 30
200 | Weekly | 5 | 10 | 15 | 20 | 30
200 | Biweekly | 10 | 20 | 30 | 40 | 60
n/a, not applicable.

For example, if a patient with a body weight of 70 kg has an actual IgG trough level of 900 mg/dL and the target trough level is 1000 mg/dL, this results in a difference of 100 mg/dL. Therefore, increase the weekly dose of HIZENTRA by 10 mL. For biweekly dosing, increase the biweekly dose by 20 mL. For 2 times per week dosing, increase the dose by 5 mL.

Monitor the patient's clinical response, and repeat the dose adjustment as needed.

Dosage requirements for patients switching to HIZENTRA from another IGSC product: If a patient on HIZENTRA does not maintain an adequate clinical response or a serum IgG trough level equivalent to that of the previous IGSC treatment, the physician may want to adjust the dose. For such patients, Table 1 also provides guidance for dose adjustment if their desired IGSC trough level is known.

Measles Exposure

Administer a minimum total weekly HIZENTRA dose of 0.2 g/kg body weight for 2 consecutive weeks if a patient is at risk of measles exposure (i.e., due to an outbreak in the U.S. or travel to endemic areas outside of the U.S.). For biweekly dosing, one infusion of a minimum at 400 mg/kg is recommended. If a patient has been exposed to measles, ensure this minimum dose is administered as soon as possible after exposure.

Chronic Inflammatory Demyelinating Polyneuropathy (CIDP)

- Initiate therapy with HIZENTRA 1 week after the last IGIV infusion.
- The recommended subcutaneous dose is 0.2 g/kg (1 mL/kg) body weight per week, administered in 1 or 2 sessions over 1 or 2 consecutive days.
  - In the clinical study after transitioning from IGIV to HIZENTRA treatment, a dose of 0.4 g/kg (2 mL/kg) body weight per week was also safe and effective in preventing CIDP relapse.
- If CIDP symptoms worsen on 0.2 g/kg (1 mL/kg) body weight per week, consider increasing the HIZENTRA dose from 0.2 g/kg (1 mL/kg) to 0.4 g/kg (2 mL/kg) body weight per week, administered in 2 sessions per week over 1 or 2 consecutive days.
  - If CIDP symptoms worsen on the 0.4 g/kg body weight per week dose, consider re-initiating therapy with an IGIV product approved for treatment of CIDP, while discontinuing HIZENTRA.
- Monitor the patient's clinical response and adjust the duration of therapy based on patient need.

2.3 Administration

HIZENTRA is for subcutaneous infusion only.

HIZENTRA is intended for subcutaneous administration using an infusion pump. Infuse HIZENTRA in the abdomen, thigh, upper arm, and/or lateral hip.

- Infusion sites – A HIZENTRA dose may be infused into multiple infusion sites. Use up to 8 infusion sites in parallel. More than one infusion device can be used simultaneously. Infusion sites should be at least 2 inches apart. Change the actual site of infusion with each administration.
- Volume (as tolerated) – For the first infusion of HIZENTRA, do not exceed a volume of 15 mL per infusion site in patients with PI or up to 20 mL per infusion site in patients with CIDP. For subsequent infusions, the volume may be increased to 25 mL per infusion site for patients with PI or to 50 mL per site for patients with CIDP.
- Rate (as tolerated) – For the first infusion of HIZENTRA, the recommended flow rate is up to 15 mL per hour per infusion site in patients with PI or up to 20 mL per hour per site in patients with CIDP. For subsequent infusions, the flow rate may be increased to 25 mL per hour per site in patients with PI or up to 50 mL per hour per site in patients with CIDP.

Follow the steps below and use aseptic technique to administer HIZENTRA, either as prefilled syringe(s) or vial(s).

1. Assemble supplies Gather the HIZENTRA prefilled syringe(s) or vial(s), all supplies, and infusion log book.
2. Clean surface Clean a table or other flat surface.
3. Wash hands – Thoroughly wash and dry hands (Figure 1).
  Figure 1
4. Check prefilled syringe(s) or vial(s):
  - If using prefilled syringes, carefully peel back the transparent covering from the tray and inspect the protective cap. Peel back the outer layer of the wrap-around label to allow for viewing of HIZENTRA through the fully transparent inner layer, but don't remove the label completely (Figure 2).
    Figure 2
  - If using vials, inspect the protective cap of the vials (Figure 3).
    Figure 3

Carefully inspect each prefilled syringe(s) or vial(s) of HIZENTRA. HIZENTRA is a clear and pale yellow to light brown solution. Do not use the prefilled syringe or vial if damaged, the liquid looks cloudy, contains particles, has changed color, the protective cap of the prefilled syringe or the vial is missing or defective, or the expiration date on the label has passed.

5. Prepare HIZENTRA for infusion
  If using HIZENTRA prefilled syringes, go to Step 5.1
  If using HIZENTRA vials, go to Step 5.2
5.1 HIZENTRA prefilled syringe(s)
  - The 5 mL, 10 mL, 20 mL, and 50 mL prefilled syringes are supplied and ready to use. The 5 mL and 10 mL prefilled syringes are fully assembled (Figure 4). For the 20 mL and 50 mL prefilled syringes, screw the plunger rod onto the prefilled syringe stopper prior to use (Figure 5).
    Figure 4
    Figure 5
  - HIZENTRA prefilled syringes can be placed directly in the infusion pump if the prefilled syringe size matches the pump requirements. If the prefilled syringe can be placed directly in the infusion pump, then go to Step 6.
    NOTE:
    An additional adapter may be required for the HIZENTRA prefilled syringes to fit properly in the infusion pump. Check with the provider of your supplies for the appropriate adapter and installation instructions.
  - If the HIZENTRA prefilled syringe size does not match the infusion pump requirements, transfer the contents of the prefilled syringe to another syringe of a size specific for the infusion pump by following the directions below:
    - Use a syringe-to-syringe transfer device (tip-to-tip connector) (Figure 6) to transfer the contents of the prefilled syringe to the empty syringe specific for the infusion pump.
      Figure 6
    - Remove the protective cap from the prefilled syringe. Attach the transfer device (tip-to-tip connector) by twisting it onto the prefilled syringe. Attach the empty syringe by screwing it onto the other side of the transfer device (Figure 7).
      Figure 7
    - Make sure you transfer the amount needed to achieve the prescribed dose.
      - Measure dose from the top of the stopper
    - Push the plunger of the prefilled syringe (e.g., using your fingers, thumb or the palm of your hand) to transfer HIZENTRA from the prefilled syringe to the empty syringe.
      - Repeat this step if multiple prefilled syringes are necessary to achieve the prescribed dose. Remove the emptied prefilled syringe and attach another prefilled syringe to the transfer device (tip-to-tip connector).
    - After the transfer is complete, remove the emptied prefilled syringe and the transfer device (tip-to-tip connector) by unscrewing them from the syringe specific for your pump. Connect the filled syringe to the infusion tubing.

Go to Step 6.

5.2 Transfer HIZENTRA from vial to syringe
  - Take the protective cap off the vial (Figure 8).
    Figure 8
  - Clean the vial stopper with an alcohol wipe (Figure 9). Let the stopper dry.
    Figure 9
  - If using a transfer device, follow the instructions provided by the device manufacturer.
  - If using a needle and a syringe to transfer HIZENTRA, follow the instructions below:
    - Attach a sterile transfer needle to a sterile syringe (Figure 10).
      Figure 10
    - Pull out the plunger of the syringe to fill the syringe with air. Make sure that the amount of air is the same as the amount of HIZENTRA you will transfer from the vial.
    - Put the HIZENTRA vial on a flat surface. Keeping the vial upright, insert the transfer needle into the center of the rubber stopper.
    - Check that the tip of the needle is not in the liquid. Then, push the plunger of the syringe down. This will inject the air from the syringe into the airspace of the vial.
    - Leaving the needle in the stopper, carefully turn the vial upside down (Figure 11).
      Figure 11
    - Slowly pull back on the plunger of the syringe to fill the syringe with HIZENTRA.
    - Take the filled syringe and needle out of the stopper.
    - Take off the needle and throw it away in the sharps container.

When using multiple vials to achieve the prescribed dose, repeat this step.

6. Prepare infusion pump and tubing
  - Prior to preparing the pump(s), make sure you have the prescribed dose in the syringe(s) and the infusion tubing is attached.
  - Prepare the infusion pump following the manufacturer's instructions, including attaching any necessary adapters.
  - Do not remove the needle caps until you are ready to infuse.
    - Prime (fill) the infusion. To prime the tubing, connect the syringe filled with HIZENTRA to the infusion tubing and gently push on the syringe plunger (e.g., using your fingers or thumb or the palm of your hand) to fill the tubing with HIZENTRA (Figure 12).
      Figure 12
    - Stop priming before HIZENTRA fluid reaches the capped needle.
    - Insert the syringe filled with HIZENTRA into the infusion pump.
7. Prepare infusion site(s)
  - Select an area on your abdomen, thigh, upper arm, or side of upper leg/hip for the infusion (Figure 13).The number and location of infusion sites depends on the volume of the total dose.
    Figure 13
  - Never infuse into areas where the skin is tender, bruised, red, or hard. Avoid infusing into scars or stretch marks.
  - Infuse HIZENTRA into a maximum of 8 sites simultaneously; or up to 12 consecutively per infusion. Infusion sites should be at least 2 inches apart.
  - Clean the skin at each infusion site with an antiseptic skin prep (Figure 14). Let the skin dry.
    Figure 14
8. Insert needle(s)
  - Use just one needle per site. If injecting in more than one site, the following steps should be completed for each needle, one at a time:
  - Remove the needle cap.
  - Using 2 fingers, pinch together the skin around the infusion site. With a quick dart-like motion, insert the needle straight into the skin (Figure 15).
    Figure 15
  - Put sterile gauze and tape or a transparent dressing over the infusion site (Figure 16) to hold the needle in place.
    Figure 16
9. Start infusion
  - Follow the manufacturer's instructions to turn on the infusion pump and start the infusion (Figure 17).
    Figure 17
10. Complete infusion and record treatment (Figure 18)
  - When all the HIZENTRA has been infused, turn off the infusion pump.
  - Remove the needle(s) from the skin.
  - Once you have removed the needle(s), remove the empty syringe from the infusion pump.
  - Disconnect the infusion set from the empty syringe.
  - Cover the infusion site(s) with a protective dressing.
  - Peel-off the removable part of the label for each prefilled syringe or vial used Affix it to the patient's log book with the date and time of infusion, or scan the prefilled syringe or vial if recording the infusion electronically.
    Figure 18
11. Clean up
  - If applicable, remove adapter from the infusion pump following the manufacturer's instructions.
  - Throw away the empty HIZENTRA prefilled syringe(s) or vial(s), along with the used disposable supplies in the sharps container (Figure 19) in accordance with local requirements.
    Figure 19
  - Clean and store the infusion pump, following the manufacturer's instructions.

For self-administration, provide the patient with instructions and training for subcutaneous infusion in the home or other appropriate setting.

3 DOSAGE FORMS AND STRENGTHS

HIZENTRA is a 0.2 g/mL (20%) protein solution for subcutaneous infusion available in a single-dose, prefilled syringe (5 mL, 10 mL, 20 mL, and 50 mL) or tamper-evident vial (5 mL, 10 mL, 20 mL and 50 mL).

4 CONTRAINDICATIONS

HIZENTRA is contraindicated in patients with:

- History of anaphylactic or severe systemic reaction to human immune globulin or inactive ingredients of HIZENTRA, such as polysorbate 80.
- Hyperprolinemia Type I or II because it contains L-proline as a stabilizer [see Description (11)].
- IgA-deficiency with antibodies against IgA and a history of hypersensitivity [see Description (11)].

5 WARNINGS AND PRECAUTIONS

5.1 Hypersensitivity

Severe hypersensitivity reactions may occur to human immune globulin or components of HIZENTRA, such as polysorbate 80. If a hypersensitivity reaction occurs, discontinue the HIZENTRA infusion immediately and institute appropriate treatment.

Individuals with IgA deficiency can develop anti-IgA antibodies and anaphylactic reactions (including anaphylaxis and shock) after administration of blood components containing IgA. Patients with known antibodies to IgA may have a greater risk of developing potentially severe hypersensitivity and anaphylactic reactions with administration of HIZENTRA. HIZENTRA contains ≤50 mcg/mL IgA [see Description (11)].

5.2 Thrombosis

Thrombosis may occur following treatment with immune globulin products^1-3, including HIZENTRA. Risk factors may include: advanced age, prolonged immobilization, hypercoagulable conditions, history of venous or arterial thrombosis, use of estrogens, indwelling central vascular catheters, hyperviscosity, and cardiovascular risk factors. Thrombosis may occur in the absence of known risk factors.

Consider baseline assessment of blood viscosity in patients at risk for hyperviscosity, including those with cryoglobulins, fasting chylomicronemia/markedly high triglycerides, or monoclonal gammopathies. For patients at risk of thrombosis, administer HIZENTRA at the minimum dose and infusion rate practicable. Ensure adequate hydration in patients before administration. Monitor for signs and symptoms of thrombosis and assess blood viscosity in patients at risk for hyperviscosity [see Boxed Warning, Dosage and Administration (2) and Patient Counseling Information (17)].

5.3 Aseptic Meningitis Syndrome (AMS)

AMS has been reported with use of IGIV^4 or IGSC, including HIZENTRA. The syndrome usually begins within several hours to 2 days following immune globulin treatment. AMS is characterized by the following signs and symptoms: severe headache, nuchal rigidity, drowsiness, fever, photophobia, painful eye movements, nausea, and vomiting. Cerebrospinal fluid (CSF) studies frequently show pleocytosis up to several thousand cells per cubic millimeter, predominantly from the granulocytic series, and elevated protein levels up to several hundred mg/dL. AMS may occur more frequently in association with high doses (≥2 g/kg) and/or rapid infusion of immune globulin product.

Patients exhibiting such signs and symptoms should receive a thorough neurological examination, including CSF studies, to rule out other causes of meningitis. Discontinuation of immune globulin treatment has resulted in remission of AMS within several days without sequelae.

5.4 Renal Dysfunction/Failure

Acute renal dysfunction/failure, acute tubular necrosis, proximal tubular nephropathy, osmotic nephrosis and death may occur with use of human immune globulin products, especially those containing sucrose.^5 HIZENTRA does not contain sucrose. Ensure that patients are not volume depleted before administering HIZENTRA.

For patients judged to be at risk for developing renal dysfunction, including patients with any degree of pre-existing renal insufficiency, diabetes mellitus, age greater than 65, volume depletion, sepsis, paraproteinemia, or patients receiving known nephrotoxic drugs, monitor renal function and consider lower, more frequent dosing [see Dosage and Administration (2)].

Periodic monitoring of renal function and urine output is particularly important in patients judged to have a potential increased risk of developing acute renal failure.^6 Assess renal function, including measurement of blood urea nitrogen (BUN) and serum creatinine, before the initial infusion of HIZENTRA and at appropriate intervals thereafter. If renal function deteriorates, consider discontinuing HIZENTRA.

5.5 Hemolysis

HIZENTRA can contain blood group antibodies that may act as hemolysins and induce in vivo coating of red blood cells (RBCs) with immunoglobulin, causing a positive direct antiglobulin (Coombs') test result and hemolysis.^7,9 Delayed hemolytic anemia can develop subsequent to immune globulin therapy due to enhanced RBC sequestration, and acute hemolysis, consistent with intravascular hemolysis, has been reported.^10

Monitor recipients of HIZENTRA for clinical signs and symptoms of hemolysis. If signs and/or symptoms of hemolysis are present after HIZENTRA infusion, perform appropriate confirmatory laboratory testing.

5.6 Transfusion-Related Acute Lung Injury (TRALI)

Noncardiogenic pulmonary edema may occur in patients administered human immune globulin products.^11 TRALI is characterized by severe respiratory distress, pulmonary edema, hypoxemia, normal left ventricular function, and fever. Typically, it occurs within 1 to 6 hours following transfusion. Patients with TRALI may be managed using oxygen therapy with adequate ventilatory support.

Monitor HIZENTRA recipients for pulmonary adverse reactions. If TRALI is suspected, perform appropriate tests for the presence of anti-neutrophil antibodies in both the product and patient's serum.

5.7 Transmissible Infectious Agents

Because HIZENTRA is made from human blood, it may carry a risk of transmitting infectious agents, e.g., viruses, the variant Creutzfeldt-Jakob disease (vCJD) agent and, theoretically, the Creutzfeldt-Jakob disease (CJD) agent. This also applies to unknown or emerging viruses and other pathogens. No cases of transmission of viral diseases or CJD have been associated with the use of HIZENTRA. All infections suspected by a physician possibly to have been transmitted by HIZENTRA should be reported to CSL Behring Pharmacovigilance at 1-866-915-6958.

5.8 Laboratory Tests

Various passively transferred antibodies in immunoglobulin preparations may lead to misinterpretation of the results of serological testing.

6 ADVERSE REACTIONS

The most common adverse reactions (ARs) observed in ≥5% of study subjects receiving HIZENTRA were local reactions (e.g., swelling, redness, heat, pain, hematoma and itching at the infusion site), headache, diarrhea, fatigue, back pain, nausea, pain in extremity, cough, upper respiratory tract infection, rash, pruritus, vomiting, abdominal pain (upper), migraine, arthralgia, pain, fall and nasopharyngitis.

6.1 Clinical Trials Experience

Because clinical studies are conducted under widely varying conditions, AR rates observed in clinical studies of a product cannot be directly compared to rates in the clinical studies of another product and may not reflect the rates observed in clinical practice.

Treatment of Primary Immunodeficiency (PI)

PI U.S. Study

The safety of HIZENTRA was evaluated in a clinical study in the U.S. for 15 months (3-month wash-in/wash-out period followed by a 12-month efficacy period) in subjects with PI who had been treated previously with IGIV every 3 or 4 weeks. The safety analyses included 49 subjects in the intention-to-treat (ITT) population. The ITT population consisted of all subjects who received at least one dose of HIZENTRA [see Clinical Studies (14)].

Subjects were treated with HIZENTRA at weekly median doses ranging from 66 to 331 mg/kg body weight (mean: 181.4 mg/kg) during the wash-in/wash-out period and from 72 to 379 mg/kg (mean: 213.2 mg/kg) during the efficacy period. The 49 subjects received a total of 2264 weekly infusions of HIZENTRA.

Table 2 summarizes the most frequent adverse reactions (ARs) (experienced by at least 2 subjects) occurring during or within 72 hours after the end of an infusion. Local reactions were assessed by the investigators 15 to 45 minutes post-infusion and by the subjects 24 hours post-infusion. The investigators then evaluated the ARs arising from the subject assessments. Local reactions were the most frequent ARs observed, with infusion-site reactions (e.g., swelling, redness, heat, pain, and itching at the site of infusion) comprising 98% of local reactions.

Table 2. Incidence of Subjects with Adverse Reactions (ARs) [Excluding infections.] (Experienced by 2 or More Subjects) and Rate per Infusion (ITT Population), PI U.S. Study
 | ARs Occurring During or Within 72 Hours of Infusion
AR (≥2 Subjects) | Number (%) of Subjects (n=49) | Number (Rate [Rate of ARs per infusion.]) of ARs (n=2264 Infusions)
Local reactions [Includes infusion-site reactions as well as bruising, scabbing, pain, irritation, cysts, eczema, and nodules at the infusion site.] | 49 (100) | 1322 (0.584)
Other ARs:
Headache | 12 (24.5) | 32 (0.014)
Diarrhea | 5 (10.2) | 6 (0.003)
Fatigue | 4 (8.2) | 4 (0.002)
Back pain | 4 (8.2) | 5 (0.002)
Nausea | 4 (8.2) | 4 (0.002)
Pain in extremity | 4 (8.2) | 6 (0.003)
Cough | 4 (8.2) | 4 (0.002)
Vomiting | 3 (6.1) | 3 (0.001)
Abdominal pain, upper | 3 (6.1) | 3 (0.001)
Migraine | 3 (6.1) | 4 (0.002)
Pain | 3 (6.1) | 4 (0.002)
Arthralgia | 2 (4.1) | 3 (0.001)
Contusion | 2 (4.1) | 3 (0.001)
Rash | 2 (4.1) | 3 (0.001)
Urticaria | 2 (4.1) | 2 (<0.001)

The ratio of infusions with ARs, including local reactions, to all infusions was 1303 to 2264 (57.6%). Excluding local reactions, the corresponding ratio was 56 to 2264 (2.5%).

Table 3 summarizes infusion-site reactions based on investigator assessments 15 to 45 minutes after the end of the 683 infusions administered during regularly scheduled visits (every 4 weeks).

Table 3. Investigator Assessment [15 to 45 minutes following infusions administered at regularly scheduled visits (every 4 weeks).] of Infusion-Site Reactions by Infusion, PI U.S. Study
Infusion-Site Reaction | Number [For multiple infusion sites, every site was judged, but only the site with the strongest reaction was recorded.] (Rate [Rate of infusion-site reactions per infusion.]) of Reactions (n=683 Infusions [Number of infusions administered during regularly scheduled visits.])
Edema/induration | 467 (0.68)
Erythema | 346 (0.51)
Local heat | 108 (0.16)
Local pain | 88 (0.13)
Itching | 64 (0.09)

Most local reactions were either mild (does not interfere with routine activities [93.4%]) or moderate (interferes somewhat with routine activities and may have warranted intervention [6.3%]) in intensity.

No deaths or serious ARs occurred during the study. Two subjects withdrew from the study due to ARs. One subject experienced a severe infusion-site reaction one day after the third weekly infusion, and the other subject experienced moderate myositis.

PI European Study

In a clinical study conducted in Europe, the safety of HIZENTRA was evaluated for 10 months (3-month wash-in/wash-out period followed by a 7-month efficacy period) in 51 subjects with PI who had been treated previously with IGIV every 3 or 4 weeks or with IGSC weekly.

Subjects were treated with HIZENTRA at weekly median doses ranging from 59 to 267 mg/kg body weight (mean: 118.8 mg/kg) during the wash-in/wash-out period and from 59 to 243 mg/kg (mean: 120.1 mg/kg) during the efficacy period. The 51 subjects received a total of 1831 weekly infusions of HIZENTRA.

Table 4 summarizes the most frequent ARs (experienced by at least 2 subjects) occurring during or within 72 hours after the end of an infusion. Local reactions were assessed by the subjects between 24 and 72 hours post-infusion. The investigators then evaluated the ARs arising from the subject assessments.

Table 4. Incidence of Subjects with Adverse Reactions (ARs) [Excluding infections.] (Experienced by 2 or More Subjects) and Rate per Infusion, PI European Study
 | ARs Occurring During or Within 72 Hours of Infusion
AR (≥2 Subjects) | Number (%) of Subjects (n=51) | Number (Rate [Rate of ARs per infusion.]) of ARs (n=1831 Infusions)
Local reactions [Includes infusion-related reaction; infusion-site mass; infusion/injection-site erythema, hematoma, induration, inflammation, edema, pain, pruritus, rash, reaction, swelling; infusion-site extravasation, nodule; puncture-site reaction.] | 24 (47.1) | 105 (0.057)
Other ARs:
Headache | 9 (17.6) | 20 (0.011)
Rash | 4 (7.8) | 4 (0.002)
Pruritus | 4 (7.8) | 13 (0.007)
Fatigue | 3 (5.9) | 5 (0.003)
Abdominal pain, upper | 2 (3.9) | 3 (0.002)
Arthralgia | 2 (3.9) | 2 (0.001)
Erythema | 2 (3.9) | 4 (0.002)
Abdominal discomfort | 2 (3.9) | 3 (0.002)
Back pain | 2 (3.9) | 2 (0.001)
Hematoma | 2 (3.9) | 3 (0.002)
Hypersensitivity | 2 (3.9) | 4 (0.002)

The proportion of subjects reporting local reactions decreased over time from approximately 20% following the first infusion to <5% by the end of the study.

Three subjects withdrew from the study due to ARs of mild to moderate intensity. One subject experienced infusion-site pain and infusion-site pruritus; the second subject experienced infusion-site reaction, fatigue, and feeling cold; and the third subject experienced infusion-site reaction and hypersensitivity.

Biweekly (Every 2 Weeks) or Frequent (2 To 7 Times per Week) Dosing

No data regarding ARs are available for these alternative HIZENTRA dosing regimens because no clinical trials using these regimens were conducted.

Treatment of Chronic Inflammatory Demyelinating Polyneuropathy (CIDP)

PATH Study

The safety of 2 doses of HIZENTRA (0.2 g/kg body weight or 0.4 g/kg body weight) versus placebo was evaluated in the 24-week subcutaneous (SC) treatment period of the PATH (Polyneuropathy AND Treatment with Hizentra) study in subjects with CIDP who had been treated previously with IGIV [see Clinical Studies (14.2)]. The dose was administered once a week in 2 infusion sessions conducted on 1 or 2 consecutive day(s). The safety population included 172 subjects.

Table 5 summarizes the most frequent ARs that occurred in ≥5% of subjects treated with HIZENTRA and at a higher frequency than placebo. The overall AR rates were similar in the 0.2 g/kg body weight and 0.4 g/kg body weight HIZENTRA dose groups (50.9% and 46.6%, respectively) and higher than placebo (33.3%). The most frequent ARs were local infusion site reactions. Local reactions were more frequent among subjects who received the 0.4 g/kg body weight dose than among subjects who received the 0.2 g/kg body weight dose (29.3% and 19.3%, respectively). The exposure-adjusted rate of local reactions per subject remained greater in the 0.4 g/kg body weight dose group compared to the 0.2 g/kg body weight dose group after adjusting for the greater mean duration of exposure to HIZENTRA in the 0.4 g/kg body weight dose group (129 days) compared to that of the 0.2 g/kg body weight dose group (119 days). All local reactions were either mild (does not interfere with routine activities [94.5%]) or moderate (interferes somewhat with routine activities and may have warranted intervention [5.5%]) in intensity and the frequency tended to decrease over time. No subject withdrew because of local reaction.

One serious AR, allergic dermatitis was reported in the 0.2 g/kg body weight HIZENTRA group which started at SC Week 9 and lasted 15 days. One subject withdrew from the study due to a non-serious AR, fatigue.

Table 5. CIDP SC Treatment Period – ARs Occurring in ≥5% of Subjects Treated with HIZENTRA and at a Higher Frequency than Placebo-Treated Subjects
 | Placebo |  | 0.2 g/kg HIZENTRA |  | 0.4 g/kg HIZENTRA
 | Number (%) of Subjects n=57 | Number of Events (Rate/Infusion) n=1514 [Number of infusions.] | Number (%) of Subjects n=57 | Number of Events (Rate/Infusion) n=2007 | Number (%) of Subjects n=58 | Number of Events (Rate/Infusion) n=2218
Local Reactions [Includes infusion site erythema, infusion site swelling, infusion site pain, infusion site induration, infusion site warmth, infusion site hematoma, and infusion site pruritus.] | 4 (7.0) | 7 (0.005) | 11 (19.3) | 54 (0.027) | 17 (29.3) | 49 (0.022)
Headache | 2 (3.5) | 2 (0.001) | 4 (7.0) | 5 (0.002) | 4 (6.9) | 4 (0.002)
Nasopharyngitis | 1 (1.8) | 1 (<0.001) | 4 (7.0) | 6 (0.003) | 2 (3.4) | 2 (<0.001)
Fatigue | 1 (1.8) | 1 (<0.001) | 5 (8.8) | 5 (0.002) | 0 | 0
Upper respiratory tract infection | 2 (3.5) | 2 (0.001) | 3 (5.3) | 3 (0.001) | 2 (3.4) | 2 (<0.001)
Fall | 0 | 0 | 3 (5.3) | 8 (0.004) | 1 (1.7) | 1 (<0.001)
Back Pain | 1 (1.8) | 1 (<0.001) | 3 (5.3) | 4 (0.002) | 1 (1.7) | 1 (<0.001)
Arthralgia | 1 (1.8) | 1 (<0.001) | 3 (5.3) | 4 (0.002) | 1 (1.7) | 1 (<0.001)
Pain in Extremity | 0 | 0 | 1 (1.8) | 1 (<0.001) | 3 (5.2) | 3 (0.001)
AR = adverse reaction; SC = subcutaneous.

Hypertension was reported in 2 subjects (3.5%) in the 0.2 g/kg HIZENTRA group, 2 subjects (3.4%) in the 0.4 g/kg group, and zero subjects in the placebo group. Systemic adverse reactions in the 13-week IGIV Restabilization Period of the study for subjects also randomized and treated with HIZENTRA during the 24-week subcutaneous treatment period (N=115) occurred at a rate of 0.098 (956 infusions) relative to a rate of 0.027 (4225 infusions) during treatment with HIZENTRA in the IGSC period of the study. The systemic adverse reaction rate per infusion for HIZENTRA was 3.6-fold lower than the corresponding rate for IGIV.

The exposure-adjusted rate for systemic adverse reactions in the 13-week single-arm IGIV Restabilization Period of the study for subjects also randomized and treated with HIZENTRA during the 24-week subcutaneous treatment period (N=115) was 0.075 reactions per week, relative to an exposure-adjusted rate of 0.052 reactions per week during treatment with HIZENTRA in the IGSC period of the study. The exposure-adjusted systemic adverse reaction rate for HIZENTRA was 31% lower than the corresponding rate for IGIV. However, this difference should be interpreted with caution, because there was no parallel group of subjects receiving placebo during the period of IGIV treatment.

PATH Extension Study

The PATH Extension study was a multicenter, 48-week, open-label extension study that evaluated the long -term safety and efficacy of HIZENTRA 0.2 g/kg and 0.4 g/kg doses, per body weight, in the maintenance treatment of CIDP in subjects who either completed or were being successfully rescued from CIDP relapse with IGIV in the PATH study. A total of 82 subjects were enrolled. Of these, 66 (80.5%) subjects completed the study, and 16 (19.5%) subjects discontinued.

In the study, 30.1% of subjects in the HIZENTRA 0.2 g/kg group and 51.4% of subjects in the 0.4 g/kg group experienced adverse reactions. Similar to the PATH study, the most frequent ARs were local infusion site reactions, and local reactions were more frequent among subjects who received the 0.4 g/kg body weight dose than among subjects who received the 0.2 g/kg body weight dose (18.1% and 9.6%, respectively). Of all the local reactions, 1 subject had 3 severe reactions (interrupts routine activities or may require intensive therapeutic intervention [7.5%]) with the 0.4 g/kg dose; the rest were either mild (85.0%) or moderate (7.5%). Two subjects withdrew because of local reactions.

The total exposure was 25.1 subject years in the HIZENTRA 0.2 g/kg group and 38.7 subject years in the 0.4 g/kg group. The mean duration of exposure was 125.8 (range 1 to 330) days in the HIZENTRA 0.2 g/kg group and 196.1 (range 1 to 330) days in the 0.4 g/kg group.

6.2 Postmarketing Experience

Because postmarketing reporting of adverse reactions is voluntary and from a population of uncertain size, it is not always possible to reliably estimate the frequency of these reactions or establish a causal relationship to product exposure.

HIZENTRA

The following adverse reactions have been identified during postmarketing use of HIZENTRA. This list does not include reactions already reported in clinical studies with HIZENTRA [see Adverse Reactions (6.1)].

- Infusion reactions: Allergic-anaphylactic reactions such as swollen face or tongue and pharyngeal edema, pyrexia, chills, dizziness, hypertension/changes in blood pressure, malaise, tachycardia, flushing.
- Cardiovascular: Chest discomfort (including chest pain)
- Respiratory: Dyspnea
- Neurological: Tremor, burning sensation
- General disorders and administration site conditions: Infusion site ulcer, infusion site necrosis

Immune Globulin Products

The following adverse reactions have been reported during postmarketing use of immune globulin products:^5

- Infusion reactions: Wheezing, rigors, myalgia
- Renal: Osmotic nephropathy
- Respiratory: Apnea, Acute Respiratory Distress Syndrome (ARDS), cyanosis, hypoxemia, pulmonary edema, bronchospasm
- Cardiovascular: Cardiac arrest, vascular collapse, hypotension
- Neurological: Coma, loss of consciousness, seizures, aseptic meningitis syndrome
- Integumentary: Stevens-Johnson syndrome, epidermolysis, erythema multiforme, dermatitis (e.g., bullous dermatitis)
- Hematologic: Pancytopenia, leukopenia, hemolysis, positive direct antiglobulin (Coombs') test
- Gastrointestinal: Hepatic dysfunction

To report SUSPECTED ADVERSE REACTIONS, contact CSL Behring Pharmacovigilance at 1-866-915-6958 or FDA at 1-800-FDA-1088 or www.fda.gov/medwatch.

7 DRUG INTERACTIONS

7.1 Live Virus Vaccines

The passive transfer of antibodies with immunoglobulin administration may interfere with the response to live virus vaccines such as measles, mumps, rubella, and varicella [see Patient Counseling Information (17)].

7.2 Serological Testing

Various passively transferred antibodies in immunoglobulin preparations may lead to misinterpretation of the results of serological testing.

8 USE IN SPECIFIC POPULATIONS

8.1 Pregnancy

Risk Summary

No human data are available to indicate the presence or absence of drug-associated risk. Animal reproduction studies have not been conducted with HIZENTRA. It is not known whether HIZENTRA can cause fetal harm when administered to a pregnant woman or can affect reproduction capacity. Immune globulins cross the placenta from maternal circulation increasingly after 30 weeks of gestation. HIZENTRA should be given to pregnant women only if clearly needed. In the U.S. general population, the estimated background risk of major birth defects and miscarriage in clinically recognized pregnancies is 2-4% and 15-20%, respectively.

8.2 Lactation

Risk Summary

No human data are available to indicate the presence or absence of drug-associated risk. The developmental and health benefits of breastfeeding should be considered along with the mother's clinical need for HIZENTRA and any potential adverse effects on the breastfed infant from HIZENTRA or from the underlying maternal condition.

8.4 Pediatric Use

Treatment of Primary Immunodeficiency

Clinical Studies (Weekly Dosing)

The safety and effectiveness of weekly HIZENTRA have been established in the pediatric age groups 2 to 16. HIZENTRA was evaluated in 10 pediatric subjects with PI (3 children and 7 adolescents) in a study conducted in the U.S. [see Clinical Studies (14)] and in 23 pediatric subjects with PI (18 children and 5 adolescents) in Europe. There were no differences in the pharmacokinetics, safety and efficacy profiles as compared with adult subjects. No pediatric-specific dose requirements were necessary to achieve the desired serum IgG levels.

Pharmacokinetic Modeling and Simulation (Biweekly or more Frequent Dosing)

The biweekly (every 2 weeks) or more frequent dosing (2 to 7 times per week) regimens, developed from population PK-based modeling and simulation, included 57 pediatric subjects (32 from HIZENTRA clinical studies) [see Clinical Pharmacology (12.3)]. HIZENTRA dosing is adjusted to body weight. No pediatric-specific dose requirements are necessary for these regimens.

Safety and effectiveness of HIZENTRA in pediatric patients below the age of 2 have not been established.

Treatment of Chronic Inflammatory Demyelinating Polyneuropathy

The safety and effectiveness of HIZENTRA have not been established in patients with CIDP who are under the age of 18.

8.5 Geriatric Use

Treatment of Primary Immunodeficiency

Of the 49 subjects evaluated in the U.S. clinical study of HIZENTRA, 6 subjects were 65 years of age or older. No overall differences in safety or efficacy were observed between these subjects and subjects 18 to 65 years of age. The clinical study of HIZENTRA in Europe did not include subjects over the age of 65.

Treatment of Chronic Inflammatory Demyelinating Polyneuropathy

Of the 172 subjects evaluated in the SC treatment period of a global study (HIZENTRA vs placebo), 50 subjects were >65 years of age (34 HIZENTRA and 16 placebo subjects). No overall differences in safety or efficacy were observed between these subjects and subjects 18 to 65 years of age.

11 DESCRIPTION

HIZENTRA, Immune Globulin Subcutaneous (Human), 20% Liquid, is a ready-to-use, sterile 20% (0.2 g/mL) protein liquid preparation of polyvalent human immunoglobulin G (IgG) for subcutaneous administration. HIZENTRA is manufactured from large pools of human plasma by a combination of cold alcohol fractionation, octanoic acid fractionation, and anion exchange chromatography. The IgG proteins are not subjected to heating or to chemical or enzymatic modification. The Fc and Fab functions of the IgG molecule are retained. Fab functions tested include antigen binding capacities, and Fc functions tested include complement activation and Fc-receptor-mediated leukocyte activation (determined with complexed IgG). The IgG subclass distribution is similar to that of normal human plasma.

HIZENTRA has a purity of ≥98% IgG and a pH of 4.6 to 5.2. This product contains approximately 250 mmol/L (range: 210 to 290 mmol/L) L-proline (a nonessential amino acid) as a stabilizer, 8 to 30 mg/L polysorbate 80, and trace amounts of sodium. HIZENTRA contains ≤50 mcg/mL IgA, no carbohydrate stabilizers (e.g., sucrose, maltose) and no preservative.

Plasma units used in the manufacture of HIZENTRA are tested using FDA-licensed serological assays for hepatitis B surface antigen and antibodies to human immunodeficiency virus (HIV)-1/2 and hepatitis C virus (HCV) as well as FDA-licensed Nucleic Acid Testing (NAT) for HBV, HCV and HIV-1. All plasma units have been found to be nonreactive (negative) in these tests. In addition, the plasma has been tested for B19 virus (B19V) DNA by NAT. Only plasma that passes virus screening is used for production, and the limit for B19V in the fractionation pool is set not to exceed 10^4 IU of B19V DNA per mL.

The manufacturing process for HIZENTRA includes three steps to reduce the risk of virus transmission. Two of these are dedicated virus clearance steps: pH 4 incubation to inactivate enveloped viruses, and virus filtration to remove, by size exclusion, both enveloped and non-enveloped viruses as small as approximately 20 nanometers. In addition, a depth filtration step contributes to the virus reduction capacity.^12

These steps have been independently validated in a series of in vitro experiments for their capacity to inactivate and/or remove both enveloped and non-enveloped viruses. Table 6 shows the virus clearance during the manufacturing process for HIZENTRA, expressed as the mean log10 reduction factor (LRF).

Table 6. Virus Inactivation/Removal in HIZENTRA [The virus clearance of human parvovirus B19 was investigated experimentally at the pH 4 incubation step. The estimated LRF obtained was ≥5.6.]
 | HIV-1 | PRV | BVDV | WNV | EMCV | MVM
Virus Property
Genome | RNA | DNA | RNA | RNA | RNA | DNA
Envelope | Yes | Yes | Yes | Yes | No | No
Size (nm) | 80-100 | 120-200 | 50-70 | 50-70 | 25-30 | 18-24
Manufacturing Step | Mean LRF
pH 4 incubation | ≥5.6 | ≥6.1 | 4.6 | ≥7.8 | nt | nt
Depth filtration | ≥6.7 | ≥5.7 | 3.5±0.2 | 3.0±0.4 | 5.7±0.2 | 3.7±0.3
Virus filtration | ≥4.7 | ≥5.8 | ≥4.6 | ≥6.8 | ≥6.3 | ≥6.5
Overall Reduction (Log10 Units) | ≥17.0 | ≥17.6 | ≥12.7 | ≥17.6 | ≥12.0 | ≥10.2
HIV-1, human immunodeficiency virus type 1, a model for HIV-1 and HIV-2; PRV, pseudorabies virus, a nonspecific model for large enveloped DNA viruses (e.g., herpes virus); BVDV, bovine viral diarrhea virus, a model for hepatitis C virus; WNV, West Nile virus; EMCV, encephalomyocarditis virus, a model for hepatitis A virus; MVM, minute virus of mice, a model for a small highly resistant non-enveloped DNA virus (e.g., parvovirus); LRF, log10 reduction factor; nt, not tested; na, not applicable.

12 CLINICAL PHARMACOLOGY

12.1 Mechanism of Action

HIZENTRA supplies a broad spectrum of opsonizing and neutralizing IgG antibodies against a wide variety of bacterial and viral agents. The mechanism of action has not been fully elucidated, but may include immunomodulatory effects.

12.3 Pharmacokinetics

Treatment of Primary Immunodeficiency

Clinical Studies

The pharmacokinetics (PK) of HIZENTRA was evaluated in a PK substudy of subjects (14 adults, 1 pediatric subject aged 6 to <12 years, and 3 adolescent subjects aged 12 to <16 years) with PI participating in the 15-month efficacy and safety study [see Clinical Studies (14)]. All PK subjects were treated previously with PRIVIGEN®, Immune Globulin Intravenous (Human), 10% Liquid and were switched to weekly subcutaneous treatment with HIZENTRA. After a 3-month wash-in/wash-out period, doses were adjusted individually with the goal of providing a systemic serum IgG exposure (area under the IgG serum concentration vs time curve; AUC) not inferior to that of the previous weekly-equivalent IGIV dose. Table 7 summarizes PK parameters for subjects in the substudy following treatment with HIZENTRA and IGIV.

Table 7. Pharmacokinetics Parameters of HIZENTRA and IGIV, PI U.S. Study
 | HIZENTRA | IGIV [For IGIV: weekly-equivalent dose.] (PRIVIGEN®)
Number of subjects | 18 | 18
Dose (mg/kg)
Mean | 228 | 152
Range | 141-381 | 86-254
IgG peak levels (mg/dL)
Mean | 1616 | 2564
Range | 1090-2825 | 2046-3456
IgG trough levels (mg/dL)
Mean | 1448 | 1127
Range | 952-2623 | 702-1810
AUC [Standardized to a 7-day period.] (day × mg/dL)
Mean | 10560 | 10320
Range | 7210-18670 | 8051-15530
CL [Apparent clearance (CL/F) for HIZENTRA (F = bioavailability)] (mL/day/kg)
Mean | 2.2 | 1.3 [Based on n=25 from the U.S. PRIVIGEN PI study.]
Range | 1.2-3.7 | 0.9-2.1
AUC, area under the curve; CL, clearance.

For the 19 subjects completing the wash-in/wash-out period, the average dose adjustment for HIZENTRA was 153% (range: 126% to 187%) of the previous weekly-equivalent IGIV dose. After 12 weeks of treatment with HIZENTRA at this individually adjusted dose, the final steady-state AUC determinations were made in 18 of the 19 subjects. The geometric mean ratio of the steady-state AUCs, standardized to a weekly treatment period, for HIZENTRA vs IGIV treatment was 1.002 (range: 0.77 to 1.20) with a 90% confidence limit of 0.951 to 1.055 for the 18 subjects.

With HIZENTRA, peak serum levels are lower (1616 vs 2564 mg/dL) than those achieved with IGIV while trough levels are generally higher (1448 vs 1127 mg/dL). In contrast to IGIV administered every 3 to 4 weeks, weekly subcutaneous administration results in relatively stable steady-state serum IgG levels.^13,14 After the subjects had reached steady-state with weekly administration of HIZENTRA, peak serum IgG levels were observed after a mean of 2.9 days (range: 0 to 7 days) in 18 subjects.

Table 8 summarizes PK parameters at steady state for pediatric subjects (age groups: 6 to <12 years and 12 to <16 years) and adult subjects (≥16 years) in the European HIZENTRA study following weekly treatment [see Clinical Studies (14.1)]. Pediatric PK parameters are similar to those of adult subjects; thus no pediatric specific dose requirements are needed for HIZENTRA dosing.

Table 8. Pediatric Pharmacokinetics Parameters of HIZENTRA, PI European Study
 | Age Group | Age Group | Age Group
 | 6 to <12 years (n=9) | 12 to <16 years (n=3) | 16 to <65 years (n=11) | Total (n=23)
Dose (mg/kg)
Mean | 120 | 115 | 117 | 118
Range | 71-170 | 72-150 | 87-156 | 71-170
IgG trough levels (mg/dL)
Mean | 731 | 764 | 754 | 746
Range | 531-915 | 615-957 | 505-898 | 505-957
AUC0-7d (day × mg/dL)
Mean | 5230 | 5491 | 5452 | 5370
Range | 3890-6950 | 4480-6750 | 3860-6810 | 3860-6950
CL (mL/day/kg)
Mean | 2.19 | 2.17 | 2.30 | 2.23
Range | 1.57-3.05 | 1.38-3.34 | 1.82-3.01 | 1.38-3.34
AUC0-7d, area under the curve for the 7-day dosing interval; CL, apparent clearance (CL/F) (F = bioavailability).

Pharmacokinetic Modeling and Simulation

Biweekly (Every 2 Weeks) or more Frequent Dosing

Pharmacokinetic characterization of biweekly or more frequent dosing of HIZENTRA was undertaken using population PK-based modeling and simulation. Serum IgG concentration data consisted of 3837 samples from 151 unique pediatric and adult subjects with PI from four clinical studies of IGIV (PRIVIGEN®) and/or HIZENTRA. Of the 151 subjects, 94 were adult subjects (63 from HIZENTRA clinical studies) and 57 were pediatric subjects (32 from HIZENTRA clinical studies). Compared with weekly administration, PK modeling and simulation predicted that administration of HIZENTRA on a biweekly basis at double the weekly dose results in comparable IgG exposure [equivalent AUCs, with a slightly higher IgG peak (Cmax) and slightly lower trough (Cmin)]. In addition, PK modeling and simulation predicted that for the same total weekly dose, HIZENTRA infusions given 2, 3, 5, or 7 times per week (frequent dosing) produce IgG exposures comparable to weekly dosing [equivalent AUCs, with a slightly lower IgG peak (Cmax) and slightly higher trough (Cmin)]. Frequent dosing reduces the peak-to-trough variation in HIZENTRA serum levels, thus resulting in more sustained IgG exposures. See Table 9 (columns for AUC, Cmax and Cmin).

Dose Adjustment Factor

Using data from four clinical studies, results of model-based simulations demonstrated that weekly or biweekly HIZENTRA dosing regimens with an IGIV:IGSC dose adjustment factor of 1:1.37 adequately maintain median AUC0-28days and Cmin ratios at ≥90% of values observed with 4-weekly IGIV dosing. See Table 9 (top two rows).

Prediction of Trough Levels Following Regimen Changes

PK modeling and simulation also predicted changes in trough levels after switching from (a) monthly IGIV to weekly or biweekly HIZENTRA dosing, (b) weekly to biweekly HIZENTRA dosing, or (c) weekly to more frequent dosing. Table 9 (last column) shows the predicted changes in steady-state IgG trough levels after switching between the various dosing regimens.

Table 9. Predicted Ratios [Ratios are based on comparison of second regimen vs. first regimen.] [Median (5th, 95th percentiles)] of AUC, Cmax and Cmin and Changes in IgG Trough Levels after Switching Between IgG Dosing Regimens for Primary Humoral Immune Deficiency
IgG Dosing Regimen Switch |  | AUC | Cmax | Cmin | Predicted Change in Trough [Approximate change in trough based on predicted median Cmin ratio.]
From: | To: | AUC | Cmax | Cmin | Predicted Change in Trough [Approximate change in trough based on predicted median Cmin ratio.]
IGIV | Weekly HIZENTRA [Weekly dose based on dose adjustment factor of 1.37 when switching from IGIV.] | 0.97 (0.90, 1.04) | 0.68 (0.60, 0.76) | 1.16 (1.07, 1.26) | 16% increase
IGIV | Biweekly HIZENTRA [Biweekly dose = 2× weekly dose, based on dose adjustment factor of 1.37 when switching from IGIV.] | 0.97 (0.91, 1.04) | 0.71 (0.63, 0.78) | 1.10 (1.02, 1.18) | 10% increase
Weekly HIZENTRA | Biweekly HIZENTRA | 1.00 (0.98, 1.03) | 1.06 (1.02, 1.09) | 0.95 (0.92, 0.98) | 5% decrease
Weekly HIZENTRA | 2 times per week HIZENTRA | 1.01 (0.98, 1.03) | 0.99 (0.96, 1.02) | 1.03 (1.00, 1.06) | 3% increase
Weekly HIZENTRA | 3 times per week HIZENTRA | 1.01 (0.98, 1.03) | 0.99 (0.96, 1.02) | 1.04 (1.01, 1.07) | 4% increase
Weekly HIZENTRA | 5 times per week HIZENTRA (daily for 5 days) | 1.01 (0.98, 1.03) | 0.99 (0.97, 1.01) | 1.04 (1.01, 1.06) | 4% increase
Weekly HIZENTRA | Daily HIZENTRA (7 times per week) | 1.00 (0.98, 1.03) | 0.98 (0.95, 1.01) | 1.04 (1.02, 1.08) | 4% increase
AUC, area under the curve, calculated as AUC0-28days for the IGIV to HIZENTRA switches, AUC0-14days for the weekly to biweekly HIZENTRA switch, and AUC0-7days for weekly to more frequent HIZENTRA switches; Cmax, maximum IgG concentration; Cmin, minimum IgG concentration during a 28-day period (for the IGIV to HIZENTRA switches), a 14-day period (for the weekly to biweekly HIZENTRA switch), or a 7-day period (for the weekly to more frequent HIZENTRA switches).

PI Pediatric Pharmacokinetics

PK-based modeling and simulation results indicate that, similar to observations from the clinical study with weekly HIZENTRA dosing (Table 8), body weight-adjusted biweekly dosing accounted for age-related (>3 years) differences in clearance of HIZENTRA, thereby maintaining systemic IgG exposure (AUC values) in the therapeutic range.

Treatment of Chronic Inflammatory Demyelinating Polyneuropathy

PATH Study

In the PATH study, subjects (n=172) achieved sustained trough levels over a period of 24 weeks when receiving weekly doses of 0.2 g/kg body weight and 0.4 g/kg body weight, respectively. The mean (SD) IgG trough concentration after 24 weeks of HIZENTRA treatment in the 0.2 g/kg body weight group was 15.3 (2.57) g/L and in the 0.4 g/kg body weight group was 20.8 (3.23) g/L.

PATH Extension Study

A total of 82 subjects were enrolled in the PATH Extension study. The mean serum IgG concentration remained stable at approximately 20 g/L until Week 33, after this period it decreased to 17.1 g/L. The Week 33 decrease in IgG level matched the level in subjects being down titrated from 0.4 g/kg to 0.2 g/kg at Week 25. The mean IgG level decreased by 19% from enrollment into the extension study for subjects who remained stable after down-titrating to 0.2 g/kg versus the 0.4 g/kg dosing. The mean IgG level decreased by 27% from enrollment into the extension study for subjects who relapsed after down-titrating to 0.2 g/kg versus 0.4 g/kg dosing. The mean (SD) IgG level increased to 20.2 (3.59) g/L at the end of the study for subjects who relapsed on 0.2 g/kg and up-titrated to 0.4 g/kg dosing.

13 NONCLINICAL TOXICOLOGY

13.1 Carcinogenesis, Mutagenesis, Impairment of Fertility

No animal studies were conducted to evaluate the carcinogenic or mutagenic effects of HIZENTRA or its effects on fertility.

13.2 Animal Toxicology and/or Pharmacology

Long- and short-term memory loss was seen in juvenile rats in a study modeling hyperprolinemia. In this study, rats received daily subcutaneous injections with L-proline from day 6 to day 28 of life.^15 The daily amounts of L-proline used in this study were more than 60 times higher than the L-proline dose that would result from the administration of 400 mg/kg body weight of HIZENTRA once weekly. In unpublished studies using the same animal model (i.e., rats) dosed with the same amount of L-proline with a dosing interval relevant to IGSC treatment (i.e., on 5 consecutive days on days 9 to 13, or once weekly on days 9, 16, and 23), no effects on learning and memory were observed. The clinical relevance of these studies is not known.

14 CLINICAL STUDIES

14.1 Primary Immunodeficiency (PI)

U.S. Study

A prospective, open-label, multicenter, single-arm, clinical study conducted in the U.S. evaluated the efficacy, tolerability, and safety of HIZENTRA in 49 adult and pediatric subjects with PI. Subjects previously receiving monthly treatment with IGIV were switched to weekly subcutaneous administration of HIZENTRA for 15 months. Following a 3-month wash-in/wash-out period, subjects received a dose adjustment to achieve an equivalent AUC to their previous IGIV dose [see Clinical Pharmacology (12.3)] and continued treatment for a 12-month efficacy period. The efficacy analyses included 38 subjects in the modified intention-to-treat (MITT) population. The MITT population consisted of subjects who completed the wash-in/wash-out period and received at least one infusion of HIZENTRA during the efficacy period.

Although 5% of the administered doses could not be verified, the weekly median doses of HIZENTRA ranged from 72 to 379 mg/kg body weight during the efficacy period. The mean dose was 213.2 mg/kg, which was 149% of the previous IGIV dose.

In the study, the number of infusion sites per infusion ranged from 1 to 12. In 73% of infusions, the number of infusion sites was 4 or fewer. Up to 4 simultaneous infusion sites were permitted using 2 pumps; however, more than 4 sites could be used consecutively during one infusion. The infusion flow rate did not exceed 50 mL per hour for all infusion sites combined. During the efficacy period, the median duration of a weekly infusion ranged from 1.6 to 2.0 hours.

The study evaluated the annual rate of serious bacterial infections (SBIs), defined as bacterial pneumonia, bacteremia/septicemia, osteomyelitis/septic arthritis, bacterial meningitis, and visceral abscess. The study also evaluated the annual rate of any infections, the use of antibiotics for infection (prophylaxis or treatment), the days out of work/school/kindergarten/day care or unable to perform normal activities due to infections, hospitalizations due to infections, and serum IgG trough levels.

Table 10 summarizes the efficacy results for subjects in the efficacy period (MITT population) of the study. No subjects experienced an SBI in this study.

Table 10. Summary of Efficacy Results (MITT Population)
Number of subjects (efficacy period) | 38
Total number of subject days | 12,697
Infections
Annual rate of SBIs [Defined as bacterial pneumonia, bacteremia/septicemia, osteomyelitis/septic arthritis, bacterial meningitis, and visceral abscess.] | 0 SBIs per subject year [Upper 99% confidence limit: 0.132.]
Annual rate of any infections | 2.76 infections/subject year [95% confidence limits: 2.235; 3.370.]
Antibiotic use for infection (prophylaxis or treatment)
Number of subjects (%) | 27 (71.1)
Annual rate | 48.5 days/subject year
Total number of subject days | 12,605
Days out of work/school/kindergarten/day care or unable to perform normal activities due to infections
Number of days (%) | 71 (0.56)
Annual rate | 2.06 days/subject year
Hospitalizations due to infections
Number of days (%) | 7 (0.06) [Based on 1 subject.]
Annual rate | 0.2 days/subject year

The mean IgG trough levels increased by 24.2%, from 1009 mg/dL prior to the study to 1253 mg/dL during the efficacy period.

European Study

In a prospective, open-label, multicenter, single-arm, clinical study conducted in Europe, 51 adult and pediatric subjects with PI switched from monthly IGIV (31 subjects) or weekly IGSC (20 subjects) to weekly treatment with HIZENTRA. For the 46 subjects in the efficacy analysis, the weekly mean dose in the efficacy period was 120.1 mg/kg (range 59 to 243 mg/kg), which was 104% of the previous weekly equivalent IGIV or weekly IGSC dose.

None of the subjects had an SBI during the efficacy period, resulting in an annualized rate of 0 (upper one-sided 99% confidence limit of 0.192) SBIs per subject. The annualized rate of any infections was 5.18 infections per subject for the efficacy period.

14.2 Chronic Inflammatory Demyelinating Polyneuropathy (CIDP)

PATH Study

A multicenter, double-blind, randomized, placebo-controlled, parallel-group phase 3 study evaluated the efficacy, safety, and tolerability of 2 different weekly doses of HIZENTRA (0.4 g/kg body weight and 0.2 g/kg body weight) versus placebo in 172 adult subjects with CIDP and previously treated with IGIV (PATH study). The mean treatment duration was 129 days in the 0.4 g/kg HIZENTRA group and 118.9 days in the 0.2 g/kg HIZENTRA group (treatment duration up to 166 and 167 days in each group, respectively). Subjects generally used 4 infusion sites in parallel (maximum: 8 sites in parallel). Subjects infused an average of 20 mL per infusion site (maximum: 50 mL/site) with an infusion rate of 20 mL/h (maximum: 50 mL/h) and volumes up to 140 mL per infusion session. The infusion time was approximately 1 hour.

The main endpoint was the percentage of subjects who had a CIDP relapse or were withdrawn for any other reason during the SC Treatment Period. CIDP relapse was defined as a ≥1 point increase in adjusted Inflammatory Neuropathy Cause and Treatment [INCAT] score compared with baseline. Both HIZENTRA doses demonstrated superiority over placebo for the main endpoint (32.8% for 0.4 g/kg HIZENTRA and 38.6% for 0.2 g/kg HIZENTRA compared with 63.2% for placebo, p<0.001 or p=0.007, respectively), with no statistically significant difference between the doses. When only considering relapse, the CIDP relapse rates were 19.0% for 0.4 g/kg HIZENTRA and 33.3% for 0.2 g/kg HIZENTRA compared with 56.1% for placebo (p<0.001 or p=0.012, respectively), with no statistically significant difference between the doses. Eighty one percent (81%) and 67% of HIZENTRA-treated subjects remained relapse-free (0.4 g/kg body weight and 0.2 g/kg body weight, respectively); 44% of placebo subjects remained relapse-free for up to 24 weeks.

A Kaplan-Meier Plot of time to CIDP relapse or withdrawal for any other reason is shown in Figure 1.

Figure 1. Kaplan-Meier Plot Time to CIDP Relapse or Withdrawal for Any Other Reason

Subjects in both HIZENTRA dose groups remained relatively stable while subjects in the placebo group deteriorated in mean INCAT score, mean grip strength, mean Medical Research Council sum score, and mean Rasch-built Overall Disability Scale (R-ODS) centile score.

PATH Extension Study

The PATH Extension study was a multicenter, 48-week, open-label extension study that evaluated the long-term safety and efficacy of HIZENTRA 0.2 g/kg and 0.4 g/kg doses in the maintenance treatment of CIDP in subjects who either completed or were being successfully rescued from CIDP relapse with IGIV treatment in the PATH study.

A total of 82 subjects were enrolled. In the study, subjects who started on a HIZENTRA 0.2 g/kg dose were up-titrated to 0.4 g/kg dose if they relapsed. In the case of no relapse, subjects remained at a dose of 0.2 g/kg. Subjects who started on a HIZENTRA 0.4 g/kg dose were down-titrated to 0.2 g/kg dose after 24 weeks of treatment and subjects who relapsed on a HIZENTRA 0.2 g/kg dose were up-titrated to a 0.4 g/kg dose. Due to the study design, the same subject could have received both doses during the study; 72 subjects received doses of 0.4 g/kg, and 73 subjects received doses of 0.2 g/kg during the efficacy evaluation period.

Subjects who completed the PATH study without relapse on a 0.4 g/kg dose and initially received this dose in the PATH extension study, had a relapse rate of 5.6% (1/18 subjects). Subjects who completed the PATH study without relapse on a 0.2 g/kg dose and initially received this dose in the extension study had a relapse rate of 50% (3/6 subjects).

For all subjects who received 0.4 g/kg in the PATH Extension study, 9.7% (7/72 subjects) had a relapse. For all subjects who received 0.2 g/kg in the PATH extension study, 47.9% (35/73 subjects) had a relapse.

After down-titrating from HIZENTRA 0.4 g/kg to 0.2 g/kg, 50% (26/52) of subjects relapsed, of whom 92% (24/26) recovered after returning to HIZENTRA 0.4 g/kg. A total of 35 subjects relapsed on HIZENTRA 0.2 g/kg dose, of which 89% (31/35) subjects recovered after returning to 0.4 g/kg dose.

Both the PATH and PATH Extension studies demonstrated that HIZENTRA 0.2 g/kg or 0.4 g/kg dose was effective in preventing CIDP relapse when administered weekly with the HIZENTRA 0.4 g/kg dose more likely to prevent relapse.

15 REFERENCES

1. Dalakas MC. High-dose intravenous immunoglobulin and serum viscosity: risk of precipitating thromboembolic events. Neurology 1994;44:223-226.
2. Woodruff RK, Grigg AP, Firkin FC, Smith IL. Fatal thrombotic events during treatment of autoimmune thrombocytopenia with intravenous immunoglobulin in elderly patients. Lancet 1986;2:217-218.
3. Wolberg AS, Kon RH, Monroe DM, Hoffman M. Coagulation factor XI is a contaminant in intravenous immunoglobulin preparations. Am J Hematol 2000;65:30-34.
4. Gabor EP, Meningitis and skin reaction after intravenous immune globulin therapy. Ann Intern Med 1997:127:1130.
5. Pierce LR, Jain N. Risks associated with the use of intravenous immunoglobulin. Trans Med Rev 2003;17:241-251.
6. Cayco AV, Perazella MA, Hayslett JP. Renal insufficiency after intravenous immune globulin therapy: a report of two cases and an analysis of the literature. J Am Soc Nephrol 1997;8:1788-1793.
7. Copelan EA, Strohm PL, Kennedy MS, Tutschka PJ. Hemolysis following intravenous immune globulin therapy. Transfusion 1986;26:410-412.
8. Thomas MJ, Misbah SA, Chapel HM, Jones M, Elrington G, Newsom-Davis J. Hemolysis after high-dose intravenous Ig. Blood 1993;15:3789.
9. Wilson JR, Bhoopalam N, Fisher M. Hemolytic anemia associated with intravenous immunoglobulin. Muscle Nerve 1997;20:1142-1145.
10. Kessary-Shoham H, Levy Y, Shoenfeld Y, Lorber M, Gershon H. In vivo administration of intravenous immunoglobulin (IVIg) can lead to enhanced erythrocyte sequestration. J Autoimmun 1999;13:129-135.
11. Rizk A, Gorson KC, Kenney L, Weinstein R. Transfusion-related acute lung injury after the infusion of IVIG. Transfusion 2001;41:264-268.
12. Stucki M, Boschetti N, Schäfer W, et al. Investigations of prion and virus safety of a new liquid IVIG product. Biologicals 2008;36:239-247.
13. Smith GN, Griffiths B, Mollison D, Mollison PL. Uptake of IgG after intramuscular and subcutaneous injection. Lancet 1972;1:1208-1212.
14. Waniewski I, Gardulf A, Hammarström L. Bioavailability of γ-globulin after subcutaneous infusions in patients with common variable immunodeficiency. J Clin Immunol 1994;14:90-97.
15. Bavaresco CS, Streck EL, Netto CA, et al. Chronic hyperprolinemia provokes a memory deficit in the Morris Water Maze Task. Metabolic Brain Disease 2005;20:73-80.

16 HOW SUPPLIED/STORAGE AND HANDLING

HIZENTRA is supplied in a prefilled syringe or a tamper-evident vial containing 0.2 grams of protein per mL of preservative-free liquid. The HIZENTRA packaging components are not made with natural rubber latex.

Each product presentation includes a package insert and the following components:

Table 11: How Supplied

Prefilled Syringes:

Presentation | Carton NDC Number | Components
5 mL | 44206-456-21 | Prefilled syringe containing 1 gram of protein (NDC 44206-456-94)
10 mL | 44206-457-22 | Prefilled syringe containing 2 grams of protein (NDC 44206-457-95)
20 mL | 44206-458-24 | Prefilled syringe containing 4 grams of protein (NDC 44206-458-96) with plunger rod.
50 mL | 44206-455-25 | Prefilled syringe containing 10 grams of protein (NDC 44206-455-97) with plunger rod.

Vials:

Presentation | Carton NDC Number | Components
5 mL | 44206-451-01 | Vial containing 1 gram of protein (NDC 44206-451-90)
10 mL | 44206-452-02 | Vial containing 2 grams of protein (NDC 44206-452-91)
20 mL | 44206-454-04 | Vial containing 4 grams of protein (NDC 44206-454-92)
50 mL | 44206-455-10 | Vial containing 10 grams of protein (NDC 44206-455-93)

Storage and Handling

- Store the HIZENTRA prefilled syringe or vial in its original carton to protect it from light.
- Each prefilled syringe or vial label contains a peel-off strip with the prefilled syringe or vial size and product lot number for use in recording doses in a patient treatment record.
- When stored at room temperature (up to 25°C [77°F]), HIZENTRA is stable for up to 30 months, as indicated by the expiration date printed on the outer carton of the prefilled syringe or vial label.
- Do not shake the HIZENTRA prefilled syringe or vial.
- Do not freeze. Do not use product that has been frozen.
- Discard any unused product and all used disposable supplies after each infusion.

17 PATIENT COUNSELING INFORMATION

Advise the patient to read the FDA-approved patient labeling (Information for Patients and Instructions for Use).

Inform patients to immediately report the following signs and symptoms to their healthcare provider:

- Hypersensitivity reactions to HIZENTRA (including hives, generalized urticaria, tightness of the chest, wheezing, hypotension, and anaphylaxis) [see Warnings and Precautions (5.1)].
- Pain and/or swelling of an arm or leg with warmth over the affected area, discoloration of an arm or leg, unexplained shortness of breath, chest pain or discomfort that worsens on deep breathing, unexplained rapid pulse, or numbness or weakness on one side of the body [see Warnings and Precautions (5.2)].
- Severe headache, neck stiffness, drowsiness, fever, sensitivity to light, painful eye movements, nausea, and vomiting [see Warnings and Precautions (5.3)].
- Decreased urine output, sudden weight gain, fluid retention/edema, and/or shortness of breath [see Warnings and Precautions (5.4)].
- Fatigue, increased heart rate, yellowing of the skin or eyes, and dark-colored urine [see Warnings and Precautions (5.5)].
- Severe breathing problems, lightheadedness, drops in blood pressure, and fever [see Warnings and Precautions (5.6)].

Inform patients that because HIZENTRA is made from human blood, it may carry a risk of transmitting infectious agents, e.g., viruses, the variant Creutzfeldt-Jakob disease (vCJD) agent and, theoretically, the Creutzfeldt-Jakob disease (CJD) agent [see Warnings and Precautions (5.7) and Description (11)].

Inform patients that HIZENTRA may interfere with the response to live virus vaccines (e.g., measles, mumps, rubella, and varicella) and to notify their immunizing physician of recent therapy with HIZENTRA [see Drug Interactions (7)].

Home Treatment with Subcutaneous Administration

- If self-administration is deemed to be appropriate, ensure that the patient receives clear instructions and training on subcutaneous administration in the home or other appropriate setting and has demonstrated the ability to independently administer subcutaneous infusions.
- Ensure the patient understands the importance of adhering to their prescribed administration schedule to maintain appropriate steady IgG levels.
- Instruct patients to scan the prefilled syringe or vial if recording the infusion electronically and keep a diary/log book that includes information about each infusion such as, the time, date, dose, lot number(s) and any reactions.
- Inform the patient that mild to moderate local infusion-site reactions (e.g., swelling and redness) are a common side effect of subcutaneous therapy, but to contact their healthcare professional if a local reaction increases in severity or persists for more than a few days.
- Inform patients of the importance of having an infusion needle long enough to reach the subcutaneous tissue and of changing the actual site of infusion with each infusion. Explain that HIZENTRA is for subcutaneous infusion only.
- Inform patients to consider adjusting the infusion-site location, volume per site, and rate of infusion based on how infusions are tolerated.
- Inform patient to interrupt or terminate the HIZENTRA infusion if a hypersensitivity reaction occurs.
- Inform PI patients that they should be tested regularly to make sure they have the correct levels of HIZENTRA (IgG) in their blood. These tests may result in adjustments to the HIZENTRA dose.

Information for Patients

HIZENTRA®
(hi-ZEN-tra)
Immune Globulin Subcutaneous (Human), 20% Liquid

Information for Patients

This patient package insert summarizes important information about HIZENTRA. Please read it carefully before using this medicine. This information does not take the place of talking with your healthcare professional, and it does not include all of the important information about HIZENTRA. If you have any questions after reading this, ask your healthcare professional.

What is the most important information I should know about HIZENTRA?

HIZENTRA is supposed to be infused under your skin only. DO NOT inject HIZENTRA into a blood vessel (vein or artery).

What is HIZENTRA?

HIZENTRA is a prescription medicine used to treat primary immune deficiency (PI) and chronic inflammatory demyelinating polyneuropathy (CIDP). HIZENTRA is made from human blood. HIZENTRA contains antibodies called immunoglobulin G (IgG). People with PI get a lot of infections, and IgG fights germs (bacteria and viruses). People with CIDP have a form of autoimmune disease where it is believed the body's defenses attack the nerves and cause muscle weakness and numbness mainly in the legs and arms. IgG is believed to help protect the nerve from being attacked.

Who should NOT take HIZENTRA?

Do not take HIZENTRA if you have too much proline in your blood (called "hyperprolinemia") or if you have had reactions to polysorbate 80.

Tell your doctor if you have had a serious reaction to other immune globulin medicines or if you have been told that you also have a deficiency of the immunoglobulin called IgA.

Tell your doctor if you have a history of heart or blood vessel disease or blood clots, have thick blood, or have been immobile for some time. These things may increase your risk of having a blood clot after using HIZENTRA. Also tell your doctor what drugs you are using, as some drugs, such as those that contain the hormone estrogen (for example, birth control pills), may increase your risk of developing a blood clot.

How should I take HIZENTRA?

You will take HIZENTRA through an infusion, only under your skin. You will place up to 8 needles into different areas of your body each time you use HIZENTRA. The needles are attached to a pump with an infusion tube. For PI, you can have infusions as often as every day up to every two (2) weeks. For CIDP, infusions are given once weekly (in 1 or 2 sessions conducted on 1 day or 2 consecutive days). For weekly infusions, it can take about 1 to 2 hours to complete an infusion; however, this time may be shorter or longer depending on the dose and frequency your doctor has prescribed for you.

Instructions for using HIZENTRA are at the end of this patient package insert (see "How do I use HIZENTRA?"). Do not use HIZENTRA by yourself until you have been taught how by your doctor or healthcare professional.

What should I avoid while taking HIZENTRA?

Vaccines may not work well for you while you are taking HIZENTRA. Tell your doctor or healthcare professional that you are taking HIZENTRA before you get a vaccine.

Tell your doctor or healthcare professional if you are pregnant or plan to become pregnant, or if you are nursing.

What are possible side effects of HIZENTRA?

The most common side effects with HIZENTRA are:

- Redness, swelling, itching, and/or bruising at the infusion site
- Headache/migraine
- Nausea and/or vomiting
- Pain (including pain in the chest, back, joints, arms, legs)
- Fatigue
- Diarrhea
- Stomach ache/bloating
- Cough, cold or flu symptoms
- Rash (including hives)
- Itching
- Fever and/or chills
- Shortness of breath
- Dizziness
- Fall
- Runny or stuffy nose

Tell your doctor right away or go to the emergency room if you have hives, trouble breathing, wheezing, dizziness, or fainting. These could be signs of a bad allergic reaction.

Tell your doctor right away if you have any of the following symptoms. They could be signs of a serious problem.

- Reduced urination, sudden weight gain, or swelling in your legs. These could be signs of a kidney problem.
- Pain and/or swelling of an arm or leg with warmth over the affected area, discoloration of an arm or leg, unexplained shortness of breath, chest pain or discomfort that worsens on deep breathing, unexplained rapid pulse, or numbness or weakness on one side of the body. These could be signs of a blood clot.
- Bad headache with nausea, vomiting, stiff neck, fever, and sensitivity to light. These could be signs of a brain swelling called meningitis.
- Brown or red urine, fast heart rate, yellow skin or eyes. These could be signs of a blood problem.
- Chest pains or trouble breathing.
- Fever over 100ºF. This could be a sign of an infection.

Tell your doctor about any side effects that concern you. You can ask your doctor to give you more information that is available to healthcare professionals.

How do I use HIZENTRA?

Infuse HIZENTRA only after you have been trained by your doctor or healthcare professional. Below are step-by-step instructions to help you remember how to use HIZENTRA. Ask your doctor or healthcare professional about any instructions you do not understand.

INSTRUCTIONS FOR USE

HIZENTRA® (hi-ZEN-tra)
(Immune Globulin Subcutaneous (Human), 20% Liquid)
for subcutaneous use only

HIZENTRA is provided in a carton containing:

- Single-dose prefilled syringes (5 mL, 10 mL, 20 mL, and 50 mL) or
- Single-dose vials (5 mL, 10 mL, 20 mL, and 50 mL).

Store HIZENTRA in its original carton at room temperature until ready to use. Do not use the prefilled syringe or vial if the packaging is damaged.

Step 1: Assemble supplies

Gather the HIZENTRA prefilled syringe(s) or vial(s), all supplies, and infusion log book:

Infusion administration tubing
Subcutaneous needle or catheter sets
Syringes
Transfer device or needle(s)
Syringe-to-syringe transfer device (tip-to-tip connector)
Gauze and tape, or transparent dressing
Infusion pump and any adapters (if required)
Sharps container
Alcohol wipes
Antiseptic skin preps

Step 2: Clean surface

Clean a table or other flat surface.

Step 3: Wash hands

Thoroughly wash and dry your hands (Figure 1).

Figure 1

Step 4: Check prefilled syringe(s) or vial(s)

- If using prefilled syringes, carefully peel back the transparent covering from the tray and inspect the protective cap. Peel back the outer layer of the wrap-around label to allow for viewing of HIZENTRA through the fully transparent inner layer, but don't remove the label completely (Figure 2).
  Figure 2
- If using vials, inspect the protective cap of the vials (Figure 3).
  Figure 3

Carefully inspect each prefilled syringe(s) or vial(s) of HIZENTRA. HIZENTRA is a clear and pale yellow to light brown solution. Do not use the prefilled syringe or vial if:

- The liquid looks cloudy, contains particles, or has changed color.
- It is damaged, or the protective cap is missing or defective.
- The expiration date on the label has passed.

Step 5: Prepare HIZENTRA for infusion

- If using HIZENTRA prefilled syringes, go to Step 5.1
- If using HIZENTRA vials, go to Step 5.2

Step 5.1: HIZENTRA prefilled syringe(s)

- The 5 mL, 10 mL, 20 mL, and 50 mL prefilled syringes are supplied and ready to use. The 5 mL and 10 mL prefilled syringes are fully assembled (Figure 4). For the 20 mL and 50 mL prefilled syringes, screw the plunger rod onto the prefilled syringe stopper prior to use Figure 5).
  Figure 4
  Figure 5
- HIZENTRA prefilled syringes can be placed directly in the infusion pump if the prefilled syringe size matches the pump requirements. If the prefilled syringe can be placed directly in the infusion pump, then go to Step 6.

NOTE:
An additional adapter may be required for the HIZENTRA prefilled syringes to fit properly in the infusion pump. Check with the provider of your supplies for the appropriate adapter and installation instructions.

- If the HIZENTRA prefilled syringe size does not match the infusion pump requirements, transfer the contents of the prefilled syringe to another syringe of a size specific for the infusion pump by following the directions below:
  - Use a syringe-to-syringe transfer device (tip-to-tip connector) (Figure 6) to transfer the contents of the prefilled syringe to the empty syringe specific for the infusion pump.
    Figure 6
  - Remove the protective cap from the prefilled syringe. Attach the transfer device (tip-to-tip connector) by twisting it onto the prefilled syringe. Attach the empty syringe by screwing it onto the other side of the transfer device (Figure 7).

Figure 7

- Make sure you transfer the amount needed to achieve the prescribed dose.
  - Measure dose from the top of the stopper.
- Push the plunger of the prefilled syringe (e.g., using your fingers, thumb or the palm of your hand) to transfer HIZENTRA from the prefilled syringe to the empty syringe.
  - Repeat this step if multiple prefilled syringes are necessary to achieve the prescribed dose. Remove the emptied prefilled syringe and attach another prefilled syringe to the transfer device (tip-to-tip connector).
- After the transfer is complete, remove the emptied prefilled syringe and the transfer device (tip-to-tip connector) by unscrewing them from the syringe specific for your pump. Connect the filled syringe to the infusion tubing.

Go to Step 6.

Step 5.2: Transfer HIZENTRA from vial to syringe

- Take the protective cap off the vial (Figure 8).
  Figure 8
- Clean the vial stopper with an alcohol wipe (Figure 9). Let the stopper dry.
  Figure 9
- Attach a needle or transfer device to a syringe tip, using aseptic technique.
- If using a transfer device, follow the instructions provided by the device manufacturer.
- If using a needle and a syringe to transfer HIZENTRA, follow the instructions below:
  - Attach a sterile transfer needle to a sterile syringe (Figure 10).
    Figure 10
  - Pull out the plunger of the syringe to fill the syringe with air. Make sure the amount of air is the same as the amount of HIZENTRA you will transfer from the vial.
  - Put the HIZENTRA vial on a flat surface. Keeping the vial upright, insert the transfer needle into the center of the rubber stopper.
  - Check that the tip of the needle is not in the liquid. Push the plunger of the syringe down. This will inject the air from the syringe into the airspace of the vial.
  - Leaving the needle in the stopper, carefully turn the vial upside down (Figure 11).
    Figure 11
  - Slowly pull back on the plunger of the syringe to fill the syringe with HIZENTRA.
    - Take the filled syringe and needle out of the stopper. Take off the needle and throw it away in the sharps container.

When using multiple vials to achieve the prescribed dose, repeat this step.

Step 6: Prepare infusion pump and tubing

- Prior to preparing the pump(s), make sure you have the prescribed dose in the syringe(s) and the infusion tubing is attached.
- Prepare the infusion pump (following the manufacturer's instructions), including attaching any necessary adapters.
- Do not remove the needle caps until you are ready to infuse.
- Prime (fill) the infusion tubing. To prime the tubing, connect the syringe filled with HIZENTRA to the infusion tubing and gently push on the syringe plunger (e.g., using your fingers, thumb or the palm of your hand) to fill the tubing with HIZENTRA (Figure 12).
- Stop priming before HIZENTRA fluid reaches the capped needle.
- Insert the syringe filled with HIZENTRA into the infusion pump

Figure 12

Step 7: Prepare infusion site(s)

- Select an area on your abdomen, thigh, upper arm, or side of upper leg/hip for the infusion (Figure 13).
  Figure 13
- Use a different site with every HIZENTRA infusion. New sites should be at least 1 inch from a previous infusion site.
- Never infuse into areas where the skin is tender, bruised, red, or hard. Avoid infusing into scars or stretch marks.
- You can use up to 8 infusion sites at the same time. If you are using more than one infusion site, at the same time, be sure the infusion sites are at least 2 inches apart. More than one infusion device can be used simultaneously.
- Clean the skin at each infusion site with an antiseptic skin prep (Figure 14). Let the skin dry.
  Figure 14

Step 8: Insert needle(s)

- Use one needle per site. If injecting in more than one site, the following steps should be completed for each needle, one at a time.
- Remove the needle cap.
- Using two fingers, pinch together the skin around the infusion site. With a quick dart-like motion, insert the needle straight into the skin (Figure 15).
  Figure 15
- Put sterile gauze and tape or a transparent dressing over the infusion site (Figure 16). This will keep the needle from coming out.
  Figure 16

Step 9: Start infusion

- Follow the manufacturer's instructions to turn on the infusion pump and start the infusion (Figure 17).
  Figure 17

Step 10: Complete infusion and record treatment (Figure 18)

- When all the HIZENTRA has been infused turn off the infusion pump (if used).
- Remove the needle(s) from the skin.
- Once you have removed the needle(s), remove the empty syringe from the infusion pump. Disconnect the infusion set from the empty syringe.
- Cover the infusion site with a protective dressing.
- Peel off the removable part of the label for each prefilled syringe or vial. Put this label in your log book with the date and time of the infusion and include the exact amount of HIZENTRA that you infused. Scan the prefilled syringe or vial if recording the infusion electronically.
  Figure 18

Step 11: Clean up

- If applicable, remove adapter from the infusion pump following the manufacturer's instructions.
- Throw away the empty HIZENTRA prefilled syringe(s) or vial(s), along with the used disposable supplies, in the sharps container (Figure 19) in accordance with local requirements.
  Figure 19
- Clean and store the infusion pump, following the manufacturer's instructions.

Be sure to tell your doctor about any problems you have doing your infusions. Your doctor may ask to see your treatment diary or log book, so be sure to take it with you each time you visit the doctor's office.

Call your doctor for medical advice about side effects. You can also report side effects to FDA at 1-800-FDA-1088 or www.fda.gov/medwatch.

Manufactured by:
CSL Behring AG
Bern, Switzerland
U.S. License No. 1766

Distributed by:
CSL Behring LLC
Kankakee, IL 60901 USA

This Instructions for Use has been approved by the U.S. Food and Drug Administration.

Revised: 04/2023

PRINCIPAL DISPLAY PANEL - 5 mL Vial Carton

NDC 44206-451-01

1 g
5 mL

Immune Globulin
Subcutaneous (Human),
20% Liquid

Hizentra®

Single-dose vial

For Subcutaneous Administration
Only

Rx only

CSL Behring

PRINCIPAL DISPLAY PANEL - 10 mL Vial Carton

NDC 44206-452-02

2 g
10 mL

Immune Globulin
Subcutaneous (Human),
20% Liquid

Hizentra®

Single-dose vial

For Subcutaneous Administration
Only

Rx only

CSL Behring

PRINCIPAL DISPLAY PANEL - 20 mL Vial Carton

NDC 44206-454-04

4 g
20 mL

Immune Globulin
Subcutaneous (Human),
20% Liquid

Hizentra®

Single-dose vial

For Subcutaneous Administration
Only

Rx only

CSL Behring

PRINCIPAL DISPLAY PANEL - 50 mL Vial Carton

NDC 44206-455-10

10 g
50 mL

Immune Globulin
Subcutaneous (Human),
20% Liquid

Hizentra®

Single-dose vial

For Subcutaneous Administration
Only

Rx only

CSL Behring

PRINCIPAL DISPLAY PANEL - 5 mL Syringe Carton

NDC 44206-456-21

1 g
5 mL

Immune Globulin Subcutaneous (Human), 20% Liquid

Hizentra®

Single-dose prefilled syringe

For Subcutaneous Administration Only

Rx only

CSL Behring

PRINCIPAL DISPLAY PANEL - 10 mL Syringe Carton

NDC 44206-457-22

2 g
10 mL

Immune Globulin Subcutaneous (Human), 20% Liquid

Hizentra®

Single-dose prefilled syringe

For Subcutaneous Administration Only

Rx only

CSL Behring

PRINCIPAL DISPLAY PANEL - 20 mL Syringe Carton

NDC 44206-458-24

4 g
20 mL

Immune Globulin Subcutaneous (Human),
20% Liquid

Hizentra®

Single-dose prefilled syringe

For Subcutaneous Administration Only

Rx only

CSL Behring

PRINCIPAL DISPLAY PANEL - 50 mL Syringe Carton

NDC 44206-455-25

10 g
50 mL

Immune Globulin Subcutaneous (Human),
20% Liquid

Hizentra®

Single-dose prefilled syringe

For Subcutaneous Administration Only

Rx only

CSL Behring